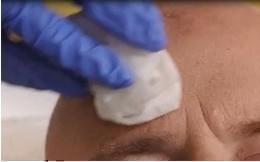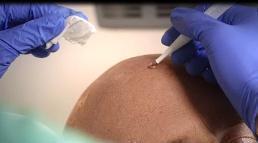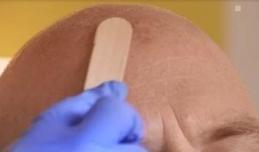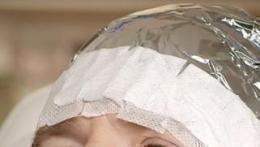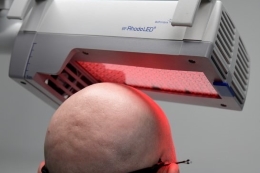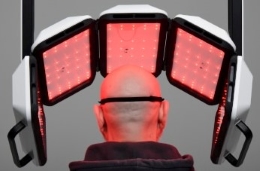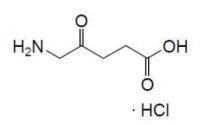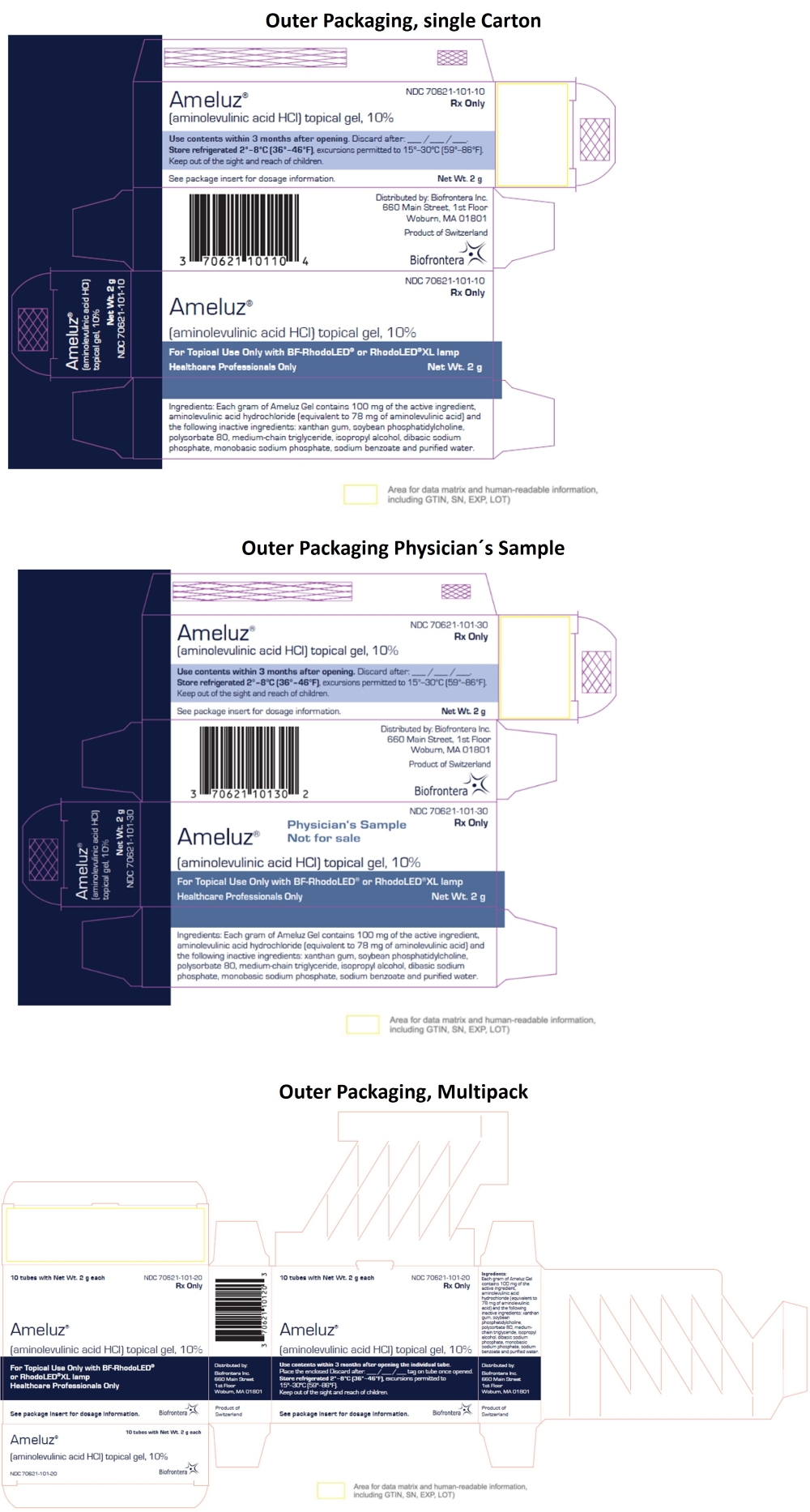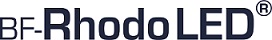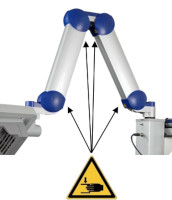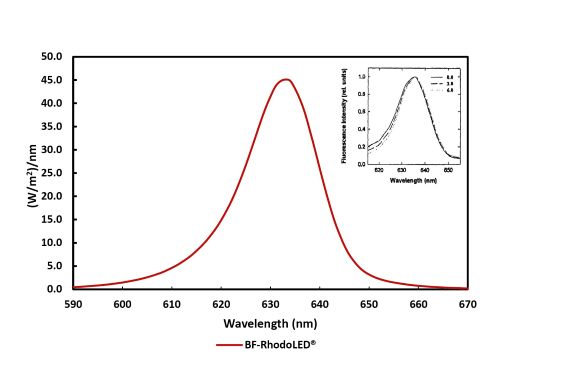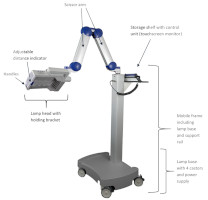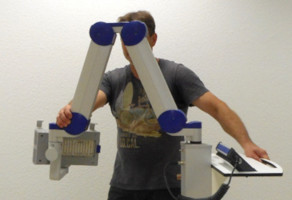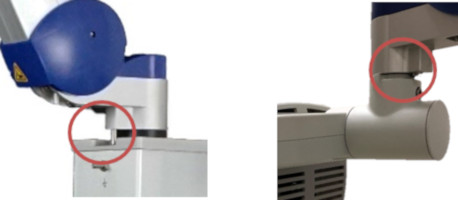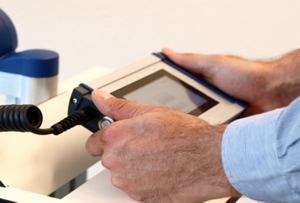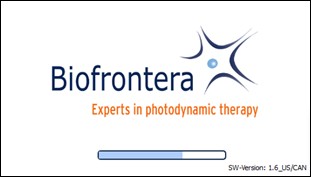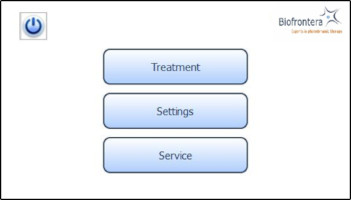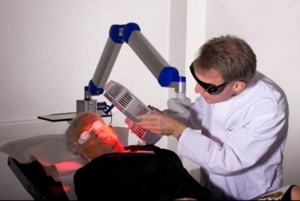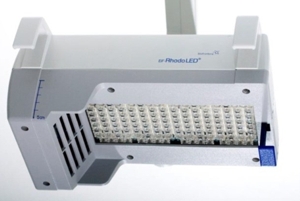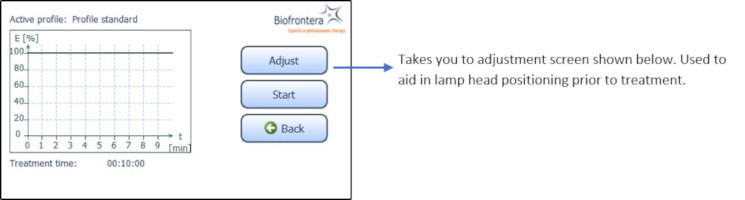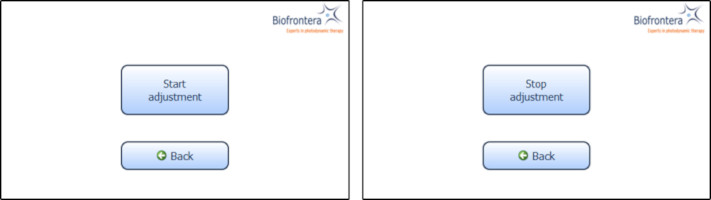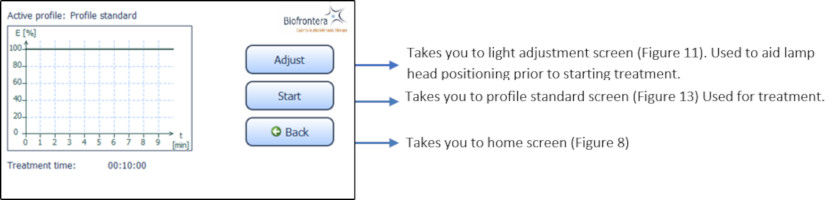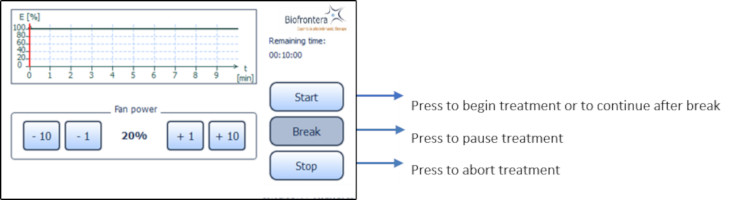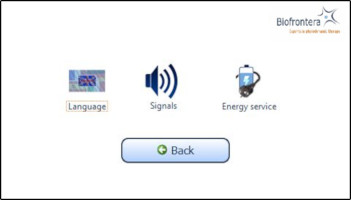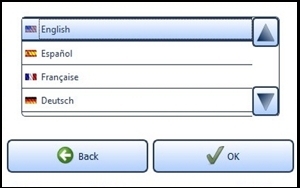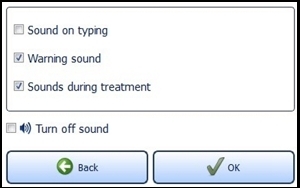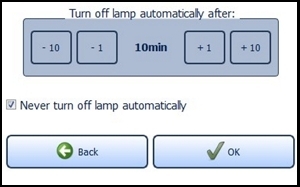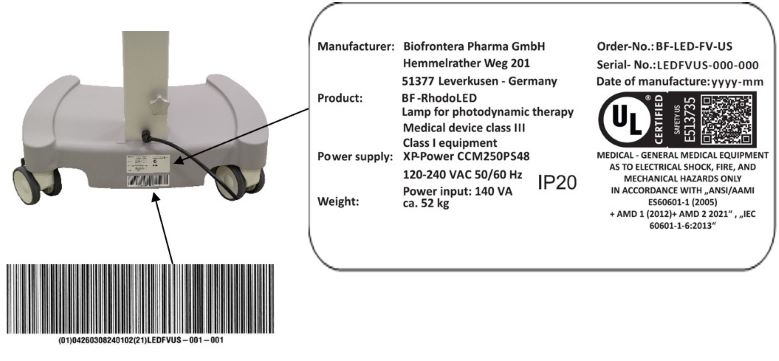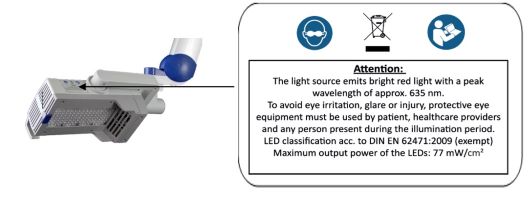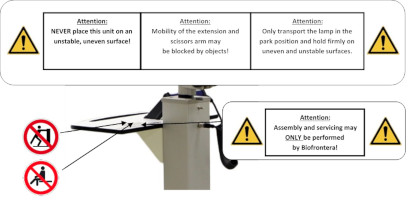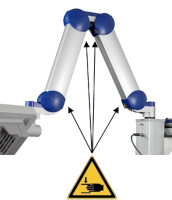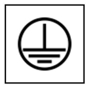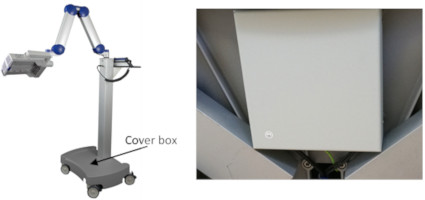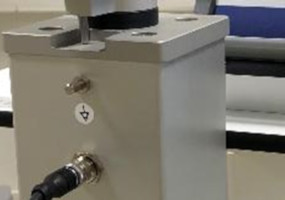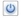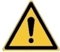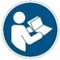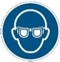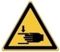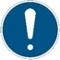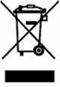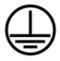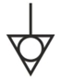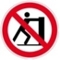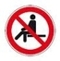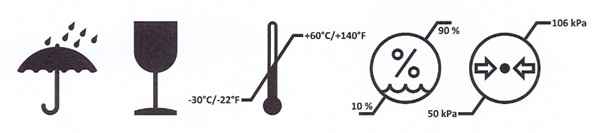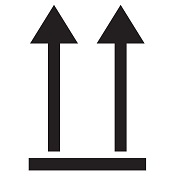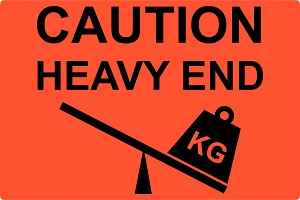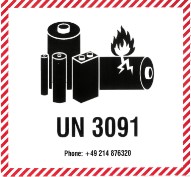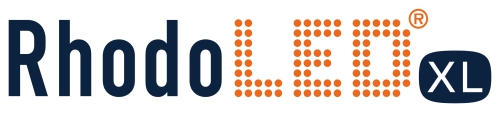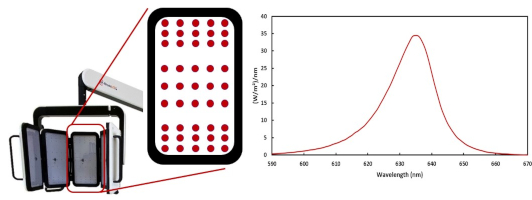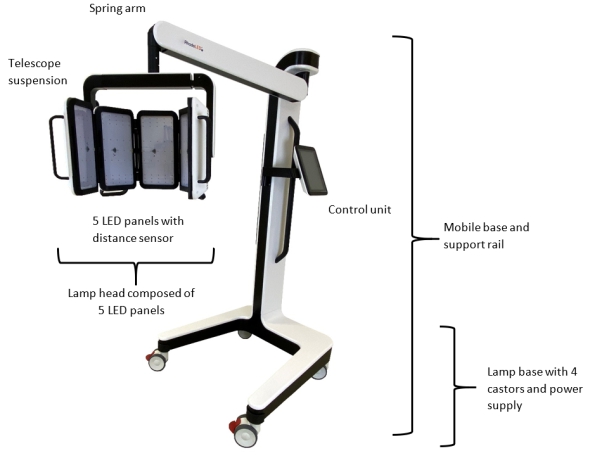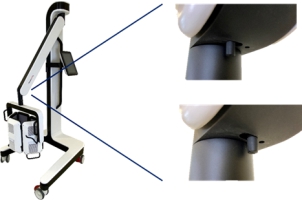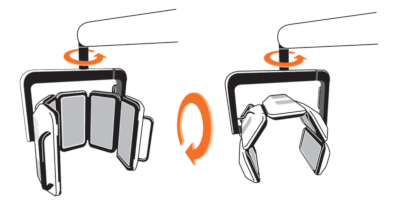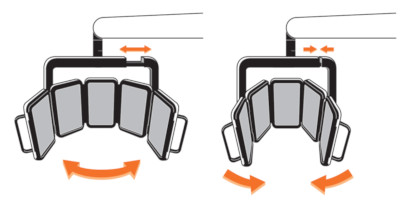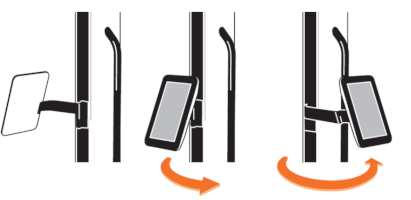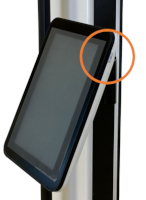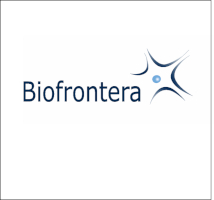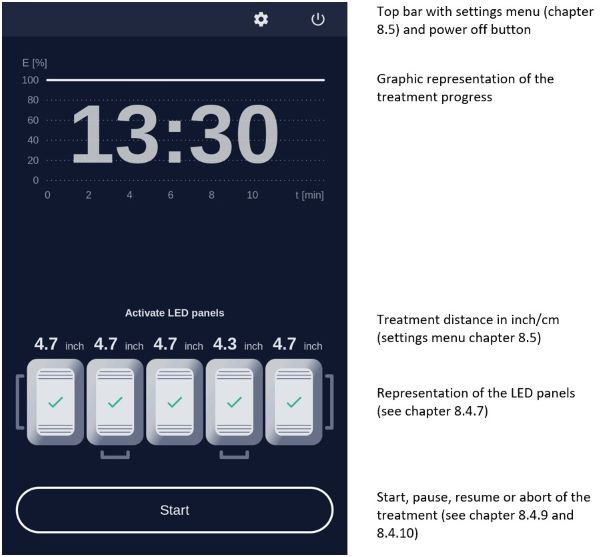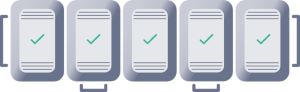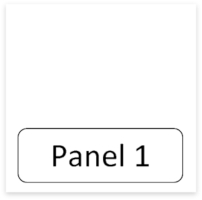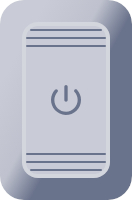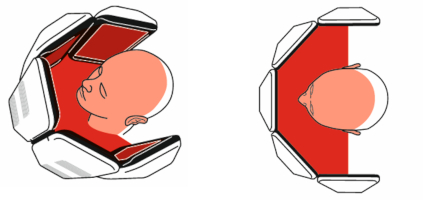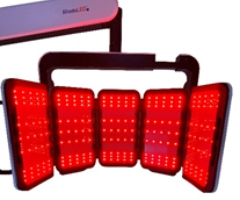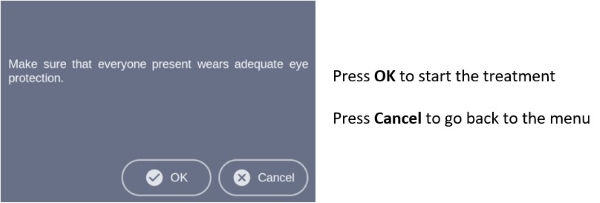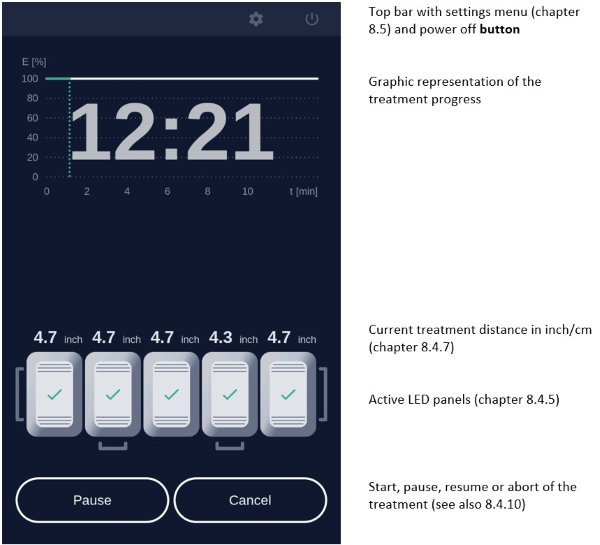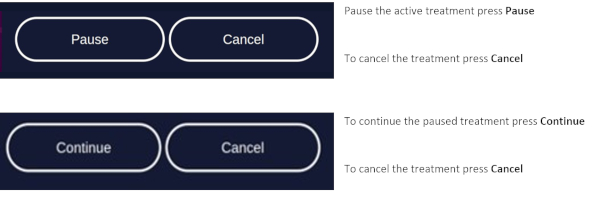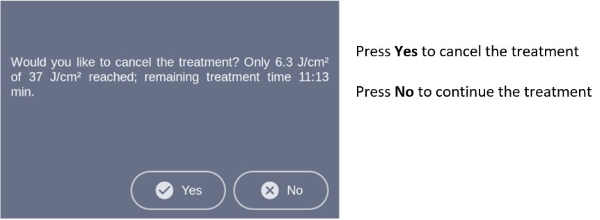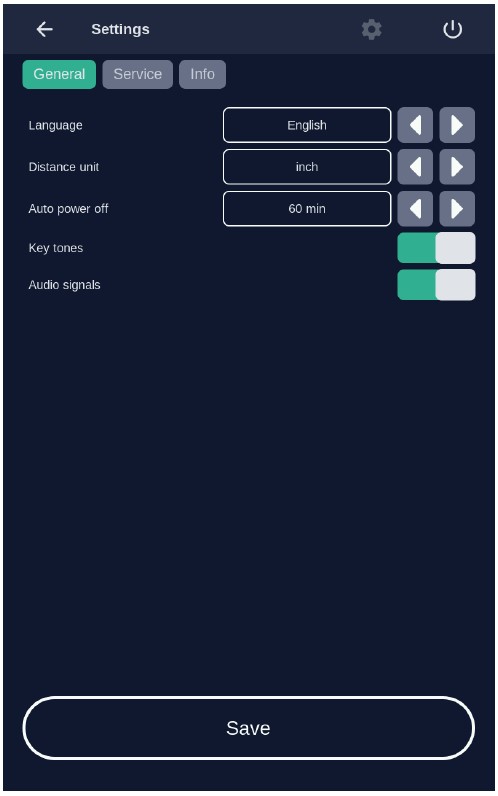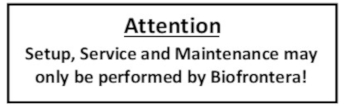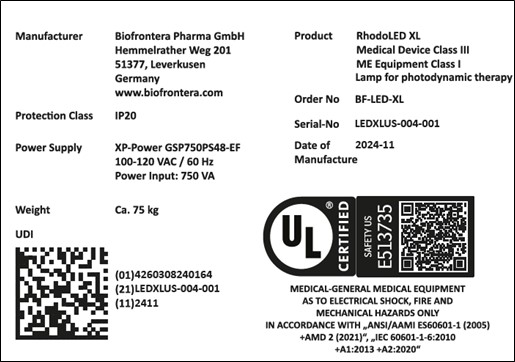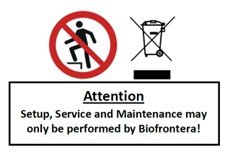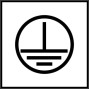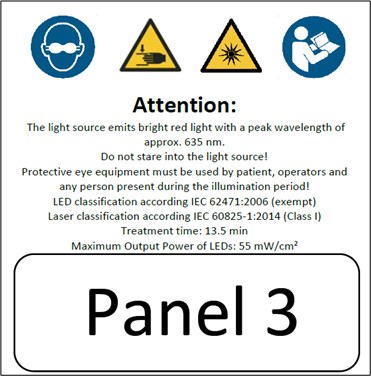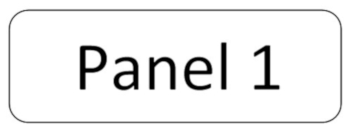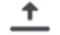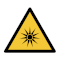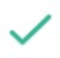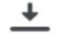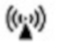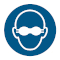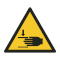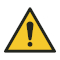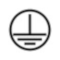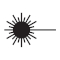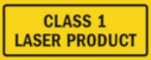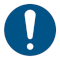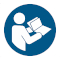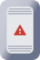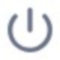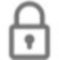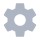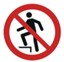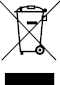 DRUG LABEL: AMELUZ
NDC: 70621-101 | Form: GEL
Manufacturer: Biofrontera Inc.
Category: prescription | Type: HUMAN PRESCRIPTION DRUG LABEL
Date: 20251222

ACTIVE INGREDIENTS: AMINOLEVULINIC ACID HYDROCHLORIDE 100 mg/1 g
INACTIVE INGREDIENTS: XANTHAN GUM; LECITHIN, SOYBEAN; POLYSORBATE 80; MEDIUM-CHAIN TRIGLYCERIDES; ISOPROPYL ALCOHOL; SODIUM PHOSPHATE, DIBASIC, DIHYDRATE; SODIUM PHOSPHATE, MONOBASIC, DIHYDRATE; SODIUM BENZOATE; WATER

HIGHLIGHTS OF PRESCRIBING INFORMATION

These highlights do not include all the information needed to use AMELUZ safely and effectively. See full prescribing information for AMELUZ.
AMELUZ® (aminolevulinic acid hydrochloride) topical gel
Initial U.S. Approval: 1999

RECENT MAJOR CHANGES

Dosage and Administration (2.2, 2.3) 10/2024

1. INDICATIONS AND USAGE

AMELUZ, a porphyrin precursor, in combination with photodynamic therapy using BF-RhodoLED or RhodoLED XL lamp, is indicated for the lesion-directed and field-directed treatment of actinic keratoses (AK) of mild-to-moderate severity on the face and scalp (1).

2. DOSAGE AND ADMINISTRATION

- Administer AMELUZ only by a health care provider (2.1).
- AMELUZ is for topical use only (2.1).
- Use AMELUZ in combination with red light photodynamic therapy (PDT). See BF-RhodoLED or RhodoLED XL user manual for detailed lamp safety and operating instructions (2.1).
- Photodynamic therapy with AMELUZ involves preparation of lesions, application of the product, occlusion and illumination with BF-RhodoLED or RhodoLED XL lamp (2.3).
- Apply an approximately 1 mm thick layer of AMELUZ to skin lesion(s). Cover individual lesions or the entire AK-field with AMELUZ. Include approximately 5 mm of the surrounding skin. Do not exceed an application area of 60 cm^2. Do not use more than 6 grams of AMELUZ (3 tubes) at one time (2.2).
- Retreat lesions that have not completely resolved 3 months after the initial treatment (2.2).

3. DOSAGE FORMS AND STRENGTHS

Gel: 10% (3).

4. CONTRAINDICATIONS

- Known hypersensitivity to porphyrins (4).
- Known hypersensitivity to any component of AMELUZ, which includes soybean phosphatidylcholine (4).
- Porphyria (4).
- Photodermatoses (4).

5. WARNINGS AND PRECAUTIONS

- Hypersensitivity: Hypersensitivity reactions have been reported with the use of AMELUZ prior to photodynamic therapy (PDT). If allergic reaction occurs, wash off AMELUZ and institute appropriate therapy (5.1).
- Transient Amnestic Episodes: Transient amnestic episodes have been reported with use of AMELUZ in combination with PDT. Advise patients to contact their healthcare provider if amnesia or confusion occurs after treatment (5.2).
- Risk of BF-RhodoLED or RhodoLED XL Lamp Induced Eye Injury: Patients and healthcare providers must wear protective eyewear before operating BF-RhodoLED or RhodoLED XL lamp (5.3).
- Ophthalmic Adverse Reactions: Avoid direct contact of AMELUZ with the eyes (5.4).
- Increased Photosensitivity: Protect treated lesions from sunlight exposure for 48 hours post treatment (5.5).
- Risk of Bleeding in Patients with Coagulation Disorders: Take special care to avoid bleeding during lesion preparation in patients with inherited or acquired coagulation disorders (5.6).
- Mucous Membrane Irritation: Avoid direct contact of AMELUZ with the mucous membranes (5.7).

6. ADVERSE REACTIONS

Most common adverse reactions (≥10%) were application site erythema, pain/burning, irritation, edema, pruritus, exfoliation, scab, induration, and vesicles (6.1).

To report SUSPECTED ADVERSE REACTIONS, contact Biofrontera Inc. at 1-844-829-7434 or FDA at 1-800-332-1088 or www.fda.gov/medwatch.

7. DRUG INTERACTIONS

Concomitant use of the following medications may enhance the phototoxic reaction to photodynamic therapy: St. John’s wort, griseofulvin, thiazide diuretics, sulfonylureas, phenothiazines, sulphonamides, quinolones, and tetracyclines (7).

FULL PRESCRIBING INFORMATION

1. INDICATIONS AND USAGE

AMELUZ, in combination with photodynamic therapy (PDT) using BF-RhodoLED® or RhodoLED® XL lamp, a narrowband, red light illumination source, is indicated for lesion-directed and field-directed treatment of actinic keratoses (AKs) of mild-to-moderate severity on the face and scalp.

2. DOSAGE AND ADMINISTRATION

2.1 Important Administration Information

AMELUZ, in conjunction with lesion preparation, is only to be administered by a health care provider.

AMELUZ is for topical use only. Not for ophthalmic, oral, or intravaginal use.

Treat single lesions or an entire field affected by multiple lesions with AMELUZ, in combination with red light photodynamic therapy (PDT). PDT requires administration of both AMELUZ and BF-RhodoLED or RhodoLED XL light.

Refer to BF-RhodoLED or RhodoLED XL user manual for detailed lamp safety and operating instructions. Adhere to all safety instructions for both patient and medical personnel while conducting the PDT.

2.2 Recommended Dosage

Apply an approximately 1-mm thick layer of AMELUZ to skin lesion(s). Cover individual lesions or the entire AK-field with AMELUZ. Include approximately 5 mm of the surrounding skin. Do not exceed an application area of 60 cm^2. Do not use more than 6 grams of AMELUZ (3 tubes) at one time.
Retreat lesions that have not completely resolved after 3 months after the initial treatment.

2.3 Administration Instructions

PDT is a multi-stage process:

Step 1. Preparation of Lesions

Before applying AMELUZ, carefully wipe all lesions with an ethanol or isopropanol-soaked cotton pad to ensure degreasing of the skin.

Figure 1A: Degreasing the skin

Thereafter, remove any scaling and crusts and gently roughen all lesion surfaces, taking care to avoid bleeding.

Figure 1B: Removal of scales and crusts

Step 2. Application of AMELUZ

Apply AMELUZ using glove protected fingertips or a spatula. Use sufficient amount of gel to cover individual lesions or the entire field:

- Lesion-directed treatment: Apply gel approximately 1 mm thick to one or more individual AK lesions and include approximately 5 mm of the surrounding healthy skin.
- Field-directed treatment: Apply gel approximately 1 mm thick to the treatment field. Apply gel to the lesions and the skin in-between the lesions. Additionally, cover approximately 5 mm of the surrounding healthy area.

Do not exceed an application area of 60 cm^2 and do not use more than 6 grams of AMELUZ (3 tubes) at one time. The gel can be applied to healthy skin around the lesions. Avoid application near mucous membranes such as the eyes, nostrils, mouth, and ears (keep a distance of 1 cm from these areas). In case of accidental contact with mucous membranes, thoroughly rinse with water [see Warnings and Precautions (5.7)].

Allow the gel to dry for approximately 10 minutes before applying occlusive dressing.

Figure 2: Drug application

Step 3. Occlusion for 3 Hours

Cover the area where the gel has been applied with a light-blocking, occlusive dressing. Following 3 hours of occlusion, remove the dressing and wipe off any remaining gel.

Figure 3: Occlusion

Step 4. Illumination with Red Light

For patient and medical personnel, wear suitable protective eyewear during illumination. Avoid staring directly into the light source [see Warnings and Precautions (5.3)].

Illuminate the treatment area with the BF-RhodoLED or RhodoLED XL lamp immediately after removing occlusion and any remaining gel. BF-RhodoLED and RhodoLED XL lamps are red light sources with a narrow spectrum around 635 nm that deliver a light dose of approximately 37 J/cm^2. Calibration by the operator is not needed; the illumination time is calculated automatically. Physical measures such as cooling with an air stream or nebulized water may help reduce pain during illumination.

Either the BF-RhodoLED or RhodoLED XL lamp can be used:

- BF-RhodoLED has an effective treatment area of 6 x 16 cm when an area of 8 x 18 cm is illuminated. Position the lamp head 5-8 cm from the skin’s surface. Larger areas can be illuminated in several steps.
- RhodoLED XL has a curved configuration with an effective treatment area up to 23 x 29 cm. Position the lamp head of the RhodoLED XL 11-14 cm from the skin’s surface. This usually allows a full-face illumination with the use of 5 panels. The smallest recommended number of panels to be used are 3 adjacent panels (see chapter 8.4.6 of RhodoLED XL user manual).

Healthy untreated skin surrounding the AK lesions does not need protection during illumination.

Figure 4A: Illumination with BF-RhodoLED

Figure 4B: Illumination with RhodoLED XL

If for any reason, the lesions cannot be illuminated within 3 hours after AMELUZ application, rinse off the gel with saline and water. For 2 days, protect the lesion sites and surrounding skin from sunlight or prolonged or intense light (e.g., tanning beds, sun lamps).

3. DOSAGE FORMS AND STRENGTHS

Topical gel: 10% aminolevulinic acid hydrochloride as a white-to-yellowish gel in 2-gram tubes.

4. CONTRAINDICATIONS

AMELUZ is contraindicated in patients with:

- Known hypersensitivity to porphyrins.
- Known hypersensitivity to any of the components of AMELUZ, which includes soybean phosphatidylcholine [see Warnings and Precautions (5.1)].
- Porphyria. AMELUZ use may cause uncontrolled phototoxic effects [see Warnings and Precautions (5.5)].
- Photodermatoses. PDT may worsen the phototoxic or photoallergic reactions [see Warnings and Precautions (5.5)].

5. WARNINGS AND PRECAUTIONS

5.1 Hypersensitivity

Several cases of hypersensitivity were reported during postmarketing use of AMELUZ prior to PDT illumination [see Adverse Reactions (6.2)]. If allergic reactions occur, clean the area of skin where the product was applied and institute appropriate therapy. Inform patients and their caregivers that AMELUZ may cause hypersensitivity, potentially including severe courses (anaphylaxis).

5.2 Transient Amnestic Episodes

Transient amnestic episodes have been reported during postmarketing use of AMELUZ in combination with photodynamic therapy. Inform patients and their caregivers that AMELUZ in combination with photodynamic therapy may cause transient amnestic episodes. Advise them to contact the healthcare provider if the patient develops amnesia after treatment.

5.3 Risk of BF-RhodoLED or RhodoLED XL Lamp Induced Eye Injury

BF-RhodoLED or RhodoLED XL lamp may cause eye irritation, glare, or injury. Before operating the lamp, personnel must refer to the user manual for specific warnings, cautions, and instructions. Eye exposure to the BF-RhodoLED or RhodoLED XL light must be prevented. Protective eye equipment must be used by patient, healthcare providers and any person present during the illumination period. Avoid staring directly into the light source.

5.4 Ophthalmic Adverse Reactions

Eyelid edema and dry eyes have occurred after PDT with AMELUZ. PDT with AMELUZ can cause ophthalmic adverse reactions. Avoid direct contact of AMELUZ with the eyes. Rinse eyes with water in case of accidental contact.

5.5 Increased Photosensitivity

AMELUZ increases photosensitivity. Avoid sunlight, prolonged or intense light (e.g., tanning beds, sun lamps) on lesions and surrounding skin treated with AMELUZ for approximately 48 hours following treatment, whether exposed to illumination or not. Concomitant use of AMELUZ with other known photosensitizing agents may increase the risk of phototoxic reaction to PDT [see Drug Interactions (7)].

5.6 Risk of Bleeding in Patients with Coagulation Disorders

AMELUZ has not been tested on patients with inherited or acquired coagulation disorders.

Take special care to avoid bleeding during lesion preparation in such patients [see Dosage and Administration (2.3)]. Any bleeding must be stopped before application of the gel.

5.7 Risk of Mucous Membrane Irritation

AMELUZ can cause mucous membrane irritation. AMELUZ is intended for topical use only. Avoid direct contact of AMELUZ to the mucous membranes. Rinse with water in case of accidental contact.

6. ADVERSE REACTIONS

The following adverse reactions are discussed in greater detail in other sections of the labeling:

- Hypersensitivity [see Warnings and Precautions (5.1)].
- Transient Amnestic Episodes [see Warnings and Precautions (5.2)].
- Risk of BF-RhodoLED or RhodoLED XL Lamp Induced Eye Injury [see Warnings and Precautions (5.3)].
- Ophthalmic Adverse Reactions [see Warnings and Precautions (5.4)].
- Increased Photosensitivity [see Warnings and Precautions (5.5)].

6.1 Clinical Trial Experience

Because clinical trials are conducted under widely varying conditions, adverse reaction rates observed in the clinical trials of a drug cannot be directly compared to rates in the clinical trials of another drug and may not reflect the rates observed in practice.

The clinical program for AMELUZ included three double-blind and placebo-controlled phase 3 trials (Trials 1, 2, and 3), enrolling a total of 299 subjects that were treated with narrow band light. Trial subjects were adults greater than or equal to 49 years of age, and the majority had Fitzpatrick skin type I, II, or III. No subjects had Fitzpatrick skin type V or VI. Approximately 86% of subjects were male, and all subjects were White.

For all three phase 3 trials, the enrolled subjects had mild to moderate AKs (Olsen grade 1 and 2) with 4 to 8 lesions on the face and scalp. Overall, 212 AMELUZ-treated subjects (n=32, n=55, and n=125) and 87 subjects receiving placebo (n=16, n=32, n=39) were illuminated with BF-RhodoLED or similar narrow spectrum lamps. For these trials, the maximal dose was one tube of AMELUZ (2 g) and the size of the application area was up to 20 cm^2.

Local skin reactions at the application site were observed in about 99.5% of subjects treated with AMELUZ and narrow spectrum lamps. The most frequent adverse reactions during and after PDT were application site erythema, pain, burning, irritation, edema, pruritus, exfoliation, scab, induration, and vesicles.

Most adverse reactions occurred during illumination or shortly afterwards, were generally of mild or moderate intensity, and lasted for 1 to 4 days in most cases; in some cases, however, they persisted for 1 to 2 weeks or even longer. Severe pain/burning occurred in up to 30% of subjects. In one case, the adverse reactions required interruption or discontinuation of the illumination.

Table 1 presents the incidence of common (≥1%, <10%) and very common (≥10%) adverse reactions at the application site in randomized, multicenter trials which evaluated a maximal dose of one tube of AMELUZ (2 g) and an application area up to 20 cm^2.

Table 1: Incidence of Adverse Reactions Occurring at ≥1% of the AMELUZ Group and More Frequently than the Vehicle Group in Actinic Keratosis Trials 1, 2, and 3 at the Application Site
Adverse reaction | Vehicle n=87 | AMELUZ n=212
Adverse reactions at the application site
Erythema; Pain/Burning; Irritation; Edema; Pruritus; Exfoliation; Scab; Induration; Vesicles; Paresthesia; Hyperalgesia; Reaction; Discomfort; Erosion; Discharge; Bleeding; Pustules | 34 (39%); 26 (30%); 17 (20%); 3 (3%); 14 (16%); 4 (5%); 2 (2%); 0 (0%); 1 (1%); 2 (2%); 0 (0%); 2 (2%); 0 (0%); 0 (0%); 0 (0%); 0 (0%); 0 (0%) | 195 (92%); 195 (92%); 153 (72%); 75 (35%); 72 (34%); 41 (19%); 41 (19%); 26 (12%); 25 (12%); 18 (9%); 13 (6%); 8 (4%); 7 (3%); 6 (3%); 4 (2%); 3 (1%); 3 (1%)

Common (≥1%, <10%) adverse reactions not at the application site for AMELUZ maximal dose of one tube (2 g) and application area up to 20 cm^2 were headache, skin exfoliation, chills and eyelid edema.

Less common (≥0.1%, <1%) adverse reactions at the application site for AMELUZ maximal dose of one tube (2 g) and application area up to 20 cm^2 were hemorrhage and swelling. The adverse reactions not at the application site were blister, feeling hot, pruritus, pyrexia, scab, nervousness, pain, petechiae, rash pustular, skin erosion and ulcer.

In a clinical trial designed to investigate the sensitization potential of aminolevulinic acid with 216 healthy subjects, 13 subjects (6%) developed allergic contact dermatitis after continuous exposure for 21 days with doses of aminolevulinic acid that were higher than doses normally used in the treatment of AK.

In two open label clinical trials to evaluate safety and tolerability, 116 subjects with actinic keratosis (AK) on the face and scalp were treated with three tubes (6 g) of AMELUZ applied to a 60 cm² area. Most adverse reactions observed were consistent with those reported in trials using one tube (2 g) of AMELUZ on a 20 cm² area (see Table 1). Additional reactions which occurred in ≥1% of subjects when three tubes (6 g) of AMELUZ were applied to a 60 cm² area included dry eyes, photosensitivity, and application site discoloration, dryness, papules, and fissures.

The frequencies of certain adverse reactions at the application site in these trials—exfoliation, itching, scabbing, and erosion—were more than 10% higher with the larger dose (three tubes, 6 g) and treatment area (60 cm²) compared to the frequencies observed in the trials for the smaller dose (one tube, 2 g) and area (20 cm²). Severe application site pain was reported by 41% of the subjects treated with three tubes (6 g) on a 60 cm² area. Most cases were reported during PDT illumination. A total of 15% of subjects discontinued illumination due to adverse reactions.

6.2 Postmarketing Experience

The following adverse reactions have been reported during post-approval use of AMELUZ. Because these reactions are reported voluntarily from a population of uncertain size, it is not always possible to reliably estimate their frequency or establish a causal relationship to drug exposure.

Skin and subcutaneous tissue disorders: allergic dermatitis, application site inflammation, application site discoloration.

Eye disorders: eye irritation, diplopia, ocular hyperemia, photophobia, and blurred vision.

General disorders and administration site conditions: fatigue.

Immune System disorders: hypersensitivity.

Nervous system disorders: dysaesthesia, transient amnestic episodes.

7. DRUG INTERACTIONS

There have been no formal studies of the interaction of AMELUZ with other drugs. It is possible that concomitant use of other known photosensitizing agents such as St. John’s wort, griseofulvin, thiazide diuretics, sulfonylureas, phenothiazines, sulphonamides, quinolones and tetracyclines may enhance the phototoxic reaction to PDT [see Warnings and Precautions (5.3)].

8. USE IN SPECIFIC POPULATIONS

8.1 Pregnancy

Risk Summary

There are no available data on AMELUZ use in pregnant women to inform a drug associated risk. Animal reproduction studies were not conducted with aminolevulinic acid. Systemic absorption of aminolevulinic acid in humans is negligible following topical administration of AMELUZ under maximal clinical use conditions [see Clinical Pharmacology (12.3)]. It is not expected that maternal use of AMELUZ will result in fetal exposure to the drug.

The background risk of major birth defects and miscarriage for the indicated population are unknown. In the U.S. general population, the estimated background risk of major birth defects and miscarriage in clinically recognized pregnancies is 2% to 4% and 15% to 20%, respectively.

8.2 Lactation

Risk Summary

No data are available regarding the presence of aminolevulinic acid in human milk, the effects of aminolevulinic acid on the breastfed infant or on milk production. However, breastfeeding is not expected to result in exposure of the child to the drug due to the negligible systemic absorption of aminolevulinic acid in humans following topical administration of AMELUZ under maximal clinical use conditions [see Clinical Pharmacology (12.3)]. The developmental and health benefits of breastfeeding should be considered along with the mother’s clinical need for AMELUZ and any potential adverse effects on the breastfeeding child from AMELUZ or from the underlying maternal condition.

8.4 Pediatric Use

Safety and effectiveness in pediatric patients below the age of 18 have not been established. AK is not a condition generally seen in the pediatric population.

8.5 Geriatric Use

Of the 384 subjects exposed to AMELUZ in randomized, multicenter clinical trials, 83% (318/384) of the subjects were 65 years old and over. No overall differences in safety or effectiveness were observed between these subjects and younger subjects, but greater sensitivity of some older individuals cannot be ruled out.

11. DESCRIPTION

AMELUZ (aminolevulinic acid hydrochloride) topical gel, 10% is a non-sterile white-to-yellowish gel. The gel formulation contains a nanoemulsion.

Aminolevulinic acid, a porphyrin precursor, is a white to off-white crystalline solid. It is readily soluble in water, methanol, and dimethylformamide. Its chemical name is 5-amino-4-oxo-pentanoic acid hydrochloride, molecular weight is 167.59 and molecular formula is C5H9NO3·HCl. The structural formula of aminolevulinic acid hydrochloride is represented below:

Each gram of AMELUZ contains 100 mg of aminolevulinic acid hydrochloride (equivalent to 78 mg aminolevulinic acid) as the active ingredient and the following inactive ingredients: xanthan gum, soybean phosphatidylcholine, polysorbate 80, medium-chain triglycerides, isopropyl alcohol, dibasic sodium phosphate, monobasic sodium phosphate, sodium benzoate and purified water.

12. CLINICAL PHARMACOLOGY

12.1 Mechanism of Action

Photoactivation following topical application of AMELUZ occurs when aminolevulinic acid (prodrug) is metabolized to protoporphyrin IX (PpIX), a photoactive compound which accumulates in the skin. When exposed to red light of a suitable wavelength and energy, PpIX is activated resulting in an excited state of porphyrin molecules. In the presence of oxygen, reactive oxygen species are formed which causes damage to cellular components, and eventually destroys the cells. AMELUZ photodynamic therapy of AK lesions utilizes photoactivation of topically applied AMELUZ resulting from BF-RhodoLED or RhodoLED XL illumination, which provides a red light of narrow spectrum and a light dose of approximately 37 J/cm^2.

12.2 Pharmacodynamics

The pharmacodynamics of AMELUZ in the treatment of actinic keratosis are unknown.

12.3 Pharmacokinetics

Aminolevulinic acid acts as a prodrug to the photoactive metabolite protoporphyrin IX (PpIX).

Pharmacokinetics (PK) of aminolevulinic acid and PpIX were evaluated in two trials:

In the first trial, a single dose of one entire tube of AMELUZ (2 grams) was applied under occlusion for 3 hours followed by PDT to a total area of 20 cm^2 in 12 adult subjects with mild to moderate AK with at least 10 AK lesions on the face or forehead. The mean ± SD baseline plasma aminolevulinic acid concentration was 20.16 ± 16.53 ng/mL. In most subjects, an up to 2.5-fold increase of aminolevulinic acid plasma concentrations was observed during the first 3 hours after AMELUZ application. The mean ± SD area under the concentration time curve (AUC0-t) and maximum concentration (Cmax) for baseline corrected aminolevulinic acid (n=12) were 142.83 ± 75.50 ng·h/mL and 27.19 ± 20.02 ng/mL, respectively. The median Tmax (time at which Cmax occurred) was 3 hours.

The mean ± SD baseline plasma PpIX concentration was 3.27 ± 2.40 ng/mL (n=12). The majority (about 55%) of the PpIX concentrations were below the limit of quantification (LOQ = 1 ng/mL) and baseline corrected values were negative in all subjects except for one. The baseline corrected AUC0-t and Cmax in the single subject was 0.07 ng·h/mL and 0.29 ng/mL, respectively.

In the second trial, a single dose of three entire tubes of AMELUZ (6 grams) was applied under occlusion for 3 hours followed by PDT to a total area of 60 cm^2 in 16 adult subjects with mild to severe AK with at least 12 AK lesions on the face and scalp. The mean ± SD baseline plasma aminolevulinic acid concentration was 13.53 ± 1.58 ng/mL. In most subjects, an up to 2.5-fold increase of aminolevulinic acid plasma concentrations was observed during the first 3 hours after AMELUZ application. The mean ± SD area under the concentration time curve (AUC0-t) and maximum concentration (Cmax) for baseline corrected aminolevulinic acid (n=16) were 134.24 ± 87.97 ng·h/mL and 33.85 ± 21.85 ng/mL, respectively. The median Tmax (time at which Cmax occurred) was 3 hours.
The mean ± SD baseline plasma PpIX concentration was 1.93 ± 0.42 ng/mL (n=15). The mean ± SD baseline corrected Cmax of PpIX was 0.67 ± 0.78 ng/mL (n=13) with a median Tmax of 4 hours. The baseline corrected PpIX concentrations in 14 of 15 subjects were < 1 ng/mL.

13. NONCLINICAL TOXICOLOGY

13.1 Carcinogenesis, Mutagenesis, Impairment of Fertility

Long-term studies to evaluate the carcinogenic potential of AMELUZ or aminolevulinic acid have not been performed.

Aminolevulinic acid revealed no evidence of mutagenic or clastogenic potential based on the results of three in vitro genotoxicity tests (Ames assay, HPRT test in V79 cells, and Human lymphocyte chromosomal aberration assay) and one in vivo genotoxicity test (mouse micronucleus assay). These genotoxicity studies were conducted without exposure to light. There is a literature report that indicates that aminolevulinic acid may cause genotoxic effects in the presence and in the absence of activating light. These genotoxic effects are likely caused by the formation of reactive oxygen species.

Animal fertility studies have not been conducted with aminolevulinic acid because of the negligible systemic absorption of aminolevulinic acid in humans following topical administration of AMELUZ under maximal clinical use conditions.

14. CLINICAL STUDIES

The efficacy and safety of AMELUZ in combination with PDT using a narrow spectrum (red light lamp) source were evaluated in three randomized, multicenter trials (Trials 1, 2, and 3). Trials 2 and 3 were vehicle-controlled and double-blind. Trial 1 was double-blind with respect to vehicle and observer-blind regarding the active comparator arm. All clinical trials included a follow-up assessment after 6 and 12 months.

In these trials, 212 subjects with 4 to 8 mild to moderate AK lesions on the face/forehead and/or bald scalp were treated with up to one tube (2 grams) of AMELUZ on an application area up to 20 cm² and a narrow band spectrum lamp. Subjects ranged from 49 to 87 years of age (mean 71 years), and 92% had Fitzpatrick skin type I, II, or III. No subjects had Fitzpatrick skin type V or VI. Approximately 86% of subjects were male, and all subjects were White.

All sessions were comprised of lesion preparation to roughen the surface and remove crusts, application of AMELUZ with occlusion for 3 hours, and removal of the residual gel. Subsequently, the entire treatment area was illuminated with a narrow spectrum red light source, a lamp of either 630 nm or 633 nm and a light dose of approximately 37 J/cm^2. In Trial 3, illumination was performed with BF-RhodoLED, a red light source with a narrow spectrum around 635 nm and a light dose of approximately 37 J/cm^2.

In all trials, the lesions that were not completely cleared 12 weeks after the initial treatment were treated a second time with an identical regimen. In the trials, 42% (88/212) of subjects needed a second treatment.

The primary endpoint for all trials was complete clearance 12 weeks after the last PDT. The results of Trials 1, 2 and 3 are presented in Table 2.

Table 2: Complete Clearance 12 Weeks After the Last Narrow Spectrum PDT in Subjects with Actinic Keratoses in Trials 1, 2 and 3
 | AMELUZ | Vehicle
Trial 1 | 106/125 (85%) | 5/39 (13%)
Trial 2 | 27/32 (84%) | 2/16 (13%)
Trial 3 | 50/55 (91%) | 7/32 (22%)

Subjects who achieved complete clearance at 12 weeks after the last PDT entered a 12-month follow-up period. In the three trials, subjects who received AMELUZ with the narrowband PDT and achieved complete clearance 12 weeks after the last PDT had recurrence rates of 14%, 11%, and 25%, respectively (at 6 months) and 40%, 22%, and 37%, respectively (at 12 months).

Recurrence was defined as the percentage of subjects with at least one recurrent lesion during the 6-month or 12-month follow-up period in subjects with completely cleared lesions 12 weeks after the last PDT.

16. HOW SUPPLIED/STORAGE AND HANDLING

AMELUZ (aminolevulinic acid hydrochloride) topical gel, 10% is a white-to-yellowish gel. The drug product is supplied in an aluminum tube with a white, high density polyethylene (HDPE) screw cap. Each tube contains 2 g of gel.

NDC 70621-101-01 2 g tube

NDC 70621-101-10 Cardbox containing one 2 g tube

NDC 70621-101-20 Cardbox containing ten 2 g tubes

Store AMELUZ in a refrigerator, 2°C – 8°C (36°F – 46°F). Excursions permitted to 15°C – 30°C (59°F – 86°F).

After opening, AMELUZ can be stored for up to 12 weeks in a refrigerator at 2°C – 8°C (36°F – 46°F) if the tube is tightly closed.

17. PATIENT COUNSELING INFORMATION

Inform patients of the following:

Hypersensitivity

Hypersensitivity has been reported with use of AMELUZ. Inform patients and their caregivers that AMELUZ may cause hypersensitivity potentially including severe courses (anaphylaxis) [see Warnings and Precautions (5.1)].

Transient amnestic episodes have been reported with use of AMELUZ in combination with photodynamic therapy. Advise patients and their families or caregivers to contact their healthcare provider if memory impairment, confusion, or disorientation is observed [see Warnings and Precautions (5.2)].

Photosensitivity

Advise patients that for approximately 48 hours following treatment to avoid exposure to sunlight, and prolonged or intense light on the treated lesion sites and surrounding skin.

Advise patients to avoid certain medications that may enhance the phototoxic reaction to PDT [see Warnings and Precautions (5.5) and Drug Interactions (7)].

Common adverse reactions

Inform patients that treatment with AMELUZ in combination with PDT may result in adverse reactions which include local skin reactions at the application site such as erythema, pain/burning, irritation, edema, pruritus, exfoliation, induration, scab, and vesicles [see Clinical Trial Experience (6.1)].

AMELUZ, BF-RhodoLED and RhodoLED are registered trade marks of Biofrontera Pharma GmbH.

PATENT INFO

Patent 11,540,981

Distributed by:

Biofrontera Inc.

660 Main Street, 1st Floor

Woburn, MA 01801

USA

INSTRUCTION FOR USE

User Manual

Manufacturer: Biofrontera Pharma GmbH
Distributor: Biofrontera Inc.

Foreword

Thank you for choosing the BF-RhodoLED® LED lamp for your photodynamic therapy. BF-RhodoLED® has been developed in accordance with applicable technical standards to provide high energy efficiency as well as constant light emission at the desired wavelength.
Your lamp must be installed and maintained by a qualified Biofrontera technician and used only in accordance with the instructions in this manual. You may request the latest printed version covering this model from Biofrontera at any time.
Our drug Ameluz® and medical device BF-RhodoLED® have been approved in combination for photodynamic therapy; the only approved use of our lamp is in combination with Ameluz® gel. This user manual provides important BF-RhodoLED® product details, cautions and warnings, and operating instructions. For Ameluz®, please use its US prescribing information. The Ameluz® prescribing information includes information on how to use the gel along with contraindications, warnings and precautions and dosage and administration.

Thorough reading and use of both this user manual and the Ameluz® USPI is required prior to treatment.
Our combination Ameluz®/BF-RhodoLED® for photodynamic therapy is only to be used by physicians or healthcare professionals.

For further questions about Ameluz®, BF-RhodoLED® or the combination therapy please contact your sales representative or Biofrontera (Ameluz-US@biofrontera.com). See contact information below or visit us at http://www.biofrontera.us.com/

Sales representative:

Name:

Tel.:

E-mail:

Biofrontera Inc.

120 Presidential Way
Suite 330
Woburn, MA 01801
USA
Phone: (844) 426-3589

Warranty and Disclaimers
Please see the terms and conditions of your contract for this information.

Manufacturer
Biofrontera Pharma GmbH, Hemmelrather Weg 201, 51377 Leverkusen, Germany

"AMELUZ, RHODOLED and BF-RhodoLED are registered trademarks of Biofrontera Pharma GmbH.
©2024 Biofrontera Pharma GmbH. All rights reserved.”

1 Intended Use

BF-RhodoLED® is a red light emitting LED lamp which is used exclusively in combination with Ameluz® gel for lesion-directed and field-directed treatment of actinic keratoses (AKs) of mild-to-moderate severity on the face and scalp.

2 BF-RhodoLED® - General Description

BF-RhodoLED® is comprised of three main components, the lamp head, the easily adjustable scissor arm, and the mobile frame with castors for smooth transport. In addition, the lamp has a convenient touchscreen monitor, storage shelf, aids for positioning the lamp head and a variable speed patient fan that can be regulated throughout the treatment.

3 Warnings and Precautions

The BF-RhodoLED® has been developed for use in photodynamic therapy in combination with Ameluz® gel (excitation wavelength approx. 635 nm). Any other use or combination of use is prohibited.

During PDT side-effects such as application site erythema, pain, irritation, edema, pruritus, exfoliation, scab, induration and vesicles may occur. For further information please see Ameluz® USPI chapter 6.

The user manual must be read carefully prior to using the BF-RhodoLED®.

The BF-RhodoLED® may only be used by healthcare professionals who have received adequate training in its use.

To avoid eye irritation, glare, or injury, protective eye equipment must be used by patient, healthcare providers and any person present during the illumination period.

Neither the BF-RhodoLED® nor the power supply unit should be exposed to excessive mechanical stress or serviced by unauthorized personnel. Assembly and servicing may only be carried out by Biofrontera qualified professionals.

Risk of trapping fingers! The mobility of the adjustable scissor arm may be obstructed by objects placed in or near slots!

Depending on positioning, the scissor arm slots below each connecting portion of the scissor arm and to the right of the support rail can cause fingers or objects to become trapped. When transporting or adjusting the lamp please ensure that fingers or other objects are NOT placed in or near the slots (see Figure 1).

Beware of Tipping!
If the castors are in locked position, the lamp will tip over if exposed to lateral force. Leaning against the device or using it for support is not permitted.
Do not place the lamp on uneven or unstable surfaces.
Do not place heavy objects on the storage shelf (maximum load up to 8 kg) or use for sitting, leaning or pushing, as this can lead to the device tipping over.

In order to avoid the risk of electrical shock, the device may only be connected to a power supply with a grounded connection.

Neither the BF-RhodoLED® nor its touchscreen monitor may come into contact with water as this may lead to severe damage or electrical shock (exception: cleaning with a damp cloth).

The plexiglass plate on the lamp head may NOT be touched during or directly after treatment as, in the event of faulty operation, the maximum temperature can reach approx. 73 °C (163.4 °F).

Do not position the lamp so that it is difficult to unplug the power plug of the medical device. The lamp can only be disconnected from the supply grid by pulling the power plug.

The BF-RhodoLED® should be operated and housed indoors in areas with temperatures between 0°C and 40°C (32°F and 104°F), and relative humidity of 10 % to 90 %.

Medical electronic devices require special precautionary measures with regard to the electro-magnetic compatibility (EMC); to avoid elect-magnetic disturbances, please do not place the device close to other electrical devices.

There is a risk of tripping over the power cord or the lamp base. When transporting or when device is not in use, unplug and keep the power cord wound around the star knobs.

Ensure that the touchscreen monitor is always returned to the fixture intended for this purpose, located on the storage shelf. Storing the touchscreen monitor by hanging it can lead to damage to the spiral cord and the plug fitting.

The touchscreen monitor should not be exposed to strong external pressure or sharp objects.

A person trained in operation of the BF-RhodoLED® must always be present during treatment.

The device must be protected against unauthorized use.

Both the maintenance and the assembly of the BF-RhodoLED® and its components (including the opening of individual components) may only be carried out by authorized personnel. In the event of servicing or assembly being carried out by any other party, Biofrontera assumes no responsibility or liability regarding the safety or use of the device.

Figure 1: The scissor arm in parked position. Arrows indicate potential points where fingers can get trapped. (The appearance of devices from batches 001 to 003 slightly differs. Appearance and location of the labels remain unaltered).

4 BF-RhodoLED® Technical Description

4.1 Light Emitting Diodes (LEDs)

The light-field of the BF-RhodoLED® consists of a total of 128 LEDs and lenses (arranged in a rectangle), which emit a uniform, bundled, visible red light with a typical peak wavelength of approximately 635 nm. The half-band width of the lamp is 20 nm.

Figure 2: Typical emission spectrum of the LEDs of the BF-RhodoLED®. Insert: Fluorescence excitation spectrum of PPIX in cells 0, 3 and 6 mm below the tissue surface (Moan et al., 1996)

The BF-RhodoLED® LEDs are calibrated so that the skin being treated receives a light dosage of approximately 37 J/cm^2 under the following conditions:

- Illumination time of 10 minutes
- Treatment distance of 5-8 cm (Optimum 6 cm)

The illumination area of the LED lamp is 8 x 18 cm. As the intensity decreases towards the edge of this area, the effective treatment area is reduced to 6 x 16 cm.

4.2 Lamp Components

The BF-RhodoLED® LED lamp consists of the following components (Figure 3):

- Lamp head with holding bracket
- Scissor arm
- Storage shelf with control unit (touchscreen monitor)
- Mobile frame and lamp base (include support rail, castors and power supply)

Figure 3: BF-RhodoLED® main components. (The appearance of devices from batches 001 to 003 slightly differs.)

The swivel range to the left and right of the vertical rail is +/- 24°. The lamp head can be adjusted horizontally and vertically and tilted sideways. The scissor arm with internal gas springs allows seamless adjustment of the lamp head to any position.
5 Eye Protection

In order to avoid eye irritation, glare or injury, protective eye equipment must be used by patient, healthcare providers and any person present during the illumination period. Do not stare into the light source! The operator and other persons present must wear protective glasses with a visible light transmission (VLT) of approximately 10%. The patient must wear eye protection such as disposable eye protection pads or eye caps with an optical density for visible light of 6 or higher. Both options are effective and comfortable for use during treatment.
Note: Eyewear is not part of the medical device. Please carefully read any accompanying usage information before using any eye protection.

In order to avoid eye irritation, glare or injury, protective eye equipment must be used by patient, healthcare providers and any person present during the illumination period.

6 BF-RhodoLED® PDT Summarized Step-by-Step Instructions

These instructions should be used in conjunction with detailed operating instructions below (chapter 7). The section titles and numbers listed next to the instruction refer to the detailed instructions and/or descriptions that correspond with each step.
Note: Every user of the BF-RhodoLED® has to be trained in operating the device. The initial training is provided by Biofrontera during set-up of the BF-RhodoLED®. Recurrent training is not mandatory but can be provided by Biofrontera employees. Before treating a patient with Ameluz, please ensure that BF-RhodoLED® is in good working order.

STEP 1) | Plug in lamp.
STEP 2) | Turn on the lamp and wait for home screen to appear (see chapter 7.3)
STEP 3) | Check the proper functioning of the BF-RhodoLED®.
STEP 4) | Treat the affected skin area: Application, incubation and removal of the topical medication following the USPI of Ameluz®.
STEP 5) | Position patient comfortably and place protective eyewear on patient (see chapter 5).
STEP 6) | Position the lamp and adjust the lamp head over the skin area to be treated (distance 5-8 cm) (see chapter 7.5.1).
STEP 7) | Put on protective eyewear and make sure anyone remaining in the treatment room also wears protective eyewear (see chapter 5).
STEP 8) | Start treatment by pressing "Treatment" on the home screen, press "Start" on the treatment screen, and press "Start" once again in the profile screen. The illumination period of 10 minutes begins (see chapter 7.5.3). Remind the patient to remain still throughout the illumination period. If sound tone during treatment is activated, explain the beep sequence to the patient. If the patient needs a break, press "Break" on the profile standard screen. To resume treatment, press "Start" on the profile standard screen (see chapter 7.5.3). To abort the illumination, press "Stop" on the profile standard screen. Adjust fan speed as needed by patient by pressing plus or minus 1% or 10% on the profile standard screen. Stay with the patient at all times during the illumination period.
STEP 9) | At the end of the illumination period, remove patient's protective eyewear and follow further instructions in the Ameluz® USPI.

7 Detailed Operating Instructions

Note: Every user of the BF-RhodoLED® has to be trained in operating the device. The initial training is provided by Biofrontera during set-up of the BF-RhodoLED®. Recurrent training is not mandatory but can be provided by Biofrontera employees. The device must be protected against unauthorized use.

In order to avoid eye irritation, glare or injury, protective eye equipment must be used by patient, healthcare providers and any person present during the illumination period.

7.1 Transport of the lamp

The transportation of the lamp shall be done when the scissor arm is completely folded. During transportation one hand shall hold on to the support rail or storage shelf while the other hand holds the scissor arm (Figure 4).

Figure 4: Transport of the lamp. (The appearance of devices from batches 001 to 003 slightly differs.)

7.2 Movement area of the scissor arm and the lamp head

The scissor arm has a swivel range of +/- 24 degrees to the left and right. The swivel range is limited by a pin at the connection between scissor arm/ support rail and scissor arm/ lamp head (Figure 5).
The lamp head can be adjusted horizontally and vertically and tilted sideways, as it has a swivel range of +/- 90 degrees in all three dimensions.

Figure 5: Limiting pins of the scissor arm and the lamp head. (The appearance of devices from batches 001 to 003 slightly differs. Appearance and location of the labels remain unaltered.)

7.3 Turning the Lamp On or Off

Note: Before turning on the lamp, the power cord must be plugged in. After connecting, the lamp can be turned on and used following the instructions below.

The on-off switch is located on the left side of the touchscreen monitor, close to its spiral cord. With the lamp plugged in, press the button to start the device.

Important: This push button can also be used to turn the lamp off. Switching off the lamp can also be done by pressing the switch off button on the touchscreen (see chapter 7.4.2 "Home Screen").

Figure 6: Touchscreen monitor

Note: The blue LED of the push button indicates that the device is in stand-by mode.

7.4 Touchscreen Monitor and Menu

When using the touchscreen, please firmly press the center of the buttons shown on the screen to ensure it is read correctly by the software. Do not press too quickly, the input may not be read by the software. The touchscreen can be used while wearing commercially available examination gloves.

7.4.1 Start Screen

The Biofrontera corporate logo and software version are displayed during the LED lamp operating system start-up (Figure 7). The operating system takes approximately 30 seconds to load.

Figure 7: Start screen

7.4.2 Home Screen

The home screen appears after the operating system has loaded. From the home screen you can select "Treatment", "Settings" or "Service" (Figure 8). In the "Treatment" menu only one treatment profile "profile standard" is available. The illumination time and light intensity of this program are fixed (see 7.5.3 for further information). The "Settings" menu allows adjustment of language, time, date, audio signals and power saving settings (see 7.6 for further information). The "Service" menu may only be accessed by authorized personnel. You can turn the LED lamp off by pressing the button.

Figure 8: Home screen

7.5 Conducting a Treatment

Prior to treating a patient with Ameluz please ensure that BF-RhodoLED® is in good working order. Before starting a treatment, make sure the lamp is set-up in accordance with the operating instructions described in the following sections.

7.5.1 Distance Indicator

Position the lamp head over the skin area to be treated at a distance of 5-8 cm. Use the adjustable distance indicator and graduated scale bar to help measure and aid in achieving the correct distance (Figure 9).

Figure 9: Positioning of the lamp head to the treated skin area

7.5.2 Adjustment Light

To further aid positioning, use the adjustment light. On the touchscreen, press the following buttons in sequence (starting in the home screen): "Treatment" (Figure 8), "Adjust" (Figure 10) and "Start Adjustment" (Figure 11). The adjustment light shows what the field of illumination will be during treatment but at a lower intensity (6x16 cm, approx. 2.4 x 6.3 inches). When finished, press "Stop adjustment" and then "Back" (Figure 11) to return to the treatment menu (Figure 10).

Figure 10: Treatment menu

Figure 11: Start and Stop adjustment

7.5.3 Treatment Menu

Press treatment to enter the treatment menu (Figure 8). The standard illumination profile is depicted in a graph in the treatment menu. The x- and y-axis specify the treatment duration and light intensity respectively (Figure 12).

Figure 12: Treatment menu

In the treatment menu (Figure 12), press the "Start" button to access the profile standard screen.

7.5.4 Profile Standard Menu

In the profile screen menu, press "Start" to begin treatment (Figure 13). You can interrupt the treatment at any time by pressing the "Break" button. Press the "Start" button to resume the treatment. Abort the current treatment by pressing the "Stop" button.
If you press "Stop" prior to the end of the total treatment time, 10 minutes, the clock will reset and any interim treatment time will be not be saved.

After pressing "Stop" or upon completion of the full 10 minute treatment the software will automatically return you to the treatment menu.

The remaining treatment time is displayed to the right of the graph and the red vertical line within the graph indicates the time that has elapsed.

Figure 13: Profile standard

7.5.5 Audio Signals during Treatment

During treatment the patient will hear audio signals, 1 beep indicating 25 %, 2 beeps indicating 50 % and 3 beeps indicating 75 % of the PDT is completed, and upon treatment completion the lamp will stop the illumination and 4 beeps will be heard (see also chapter 7.6.2).

7.5.6 Patient fan

You can control the speed of the patient fan both before and during treatment with the plus and minus buttons, in increments of 1 % or 10 %. The patient fan continues to run when the treatment is paused ("Break"). The fan can be stopped by pressing "Stop" but be aware the treatment will also be aborted and any elapsed treatment time will not be saved.
7.6 Settings Menu

The settings menu is invoked (Figure 14) by pressing the "Settings" button in the home screen view (see Figure 12).

Figure 14: Settings menu

You can configure the following parameters in this menu:

- Language
- Signals
- Energy service (Power management)

Switch back to the home screen menu via the "Back" button.

7.6.1 Language Settings

Select a language by tapping on the desired language. Use the arrow keys to scroll through the list. Confirm the selected language with the "OK" button (Figure 15). Switch back to the settings menu without saving changes by pressing the "Back" button instead of "OK".

Figure 15: Language setting
7.6.2 Sound Settings

Activate and deactivate the audio signals for typing, warnings and sounds during the treatment. To do this, select the desired fields. A check mark means the sound is on.
Confirm with the "OK" button (Figure 16) to save your settings or close the menu via the "Back" button to discard the setting.
If "Turn off sound" is activated, all signal tones are switched off.

Important Note: Warning sounds will be emitted if an error occurs during operation of the lamp.

Figure 16: Sound setting

7.6.3 Energy Service (Power Management)

Providing the standby function is not manually deactivated via the check box "Never turn off lamp automatically" located near the bottom of the screen, the lamp will turn off after 10 minutes of non-use (Figure 17). You can change this time span in the menu "Energy service" via the plus and minus buttons. The settings are confirmed with the "OK" button and rejected with the "Back" button. In both cases you will return to the settings menu.

Figure 17: Energy management

If the configured time expires, a request appears for 10 seconds asking if you wish to prevent shut down. The LED lamp turns off automatically afterwards.

7.7 Service Menu

Authorization is required to access the service menu. Only authorized personnel can access the service menu.
8 Error Messages

The BF-RhodoLED® has an integrated monitoring function. In the event of a malfunction, an error message will appear in the message display. Possible error messages are set out in the table below.

Error message | Possible causes | Measures
Lamp overheated! | - The temperature of the surrounding environment is too high. - The ventilators or ventilator slots are blocked. - The air inlets or outlets are adversely affected. | Wait until the standard temperature has been reached. Check the ventilator and test the air inlets and outlets. Remove any visible foreign objects which may be present. In case of continuing impairment of cooling please contact your local sales representative or Biofrontera.
Lamp error! Please inform your supplier. | - Some of the LEDs have failed. | Further treatments may be carried out. However, please contact your local sales representative or Biofrontera immediately.
Communication error! | - Cable break in the touchscreen monitor spiral cord. - Poor contact between the touchscreen monitor connection plug and the conduit box. | Confirm the communication error. Treatments can be continued in the treatment menu by pressing the "Start" button. Please contact your local sales representative or Biofrontera.
Lamp not calibrated! | - The lamp is not calibrated. - Improper calibration. | The lamp has to be calibrated. Please contact your local sales representative or Biofrontera immediately.
Fehler-Nr.: 0084 Please inform your supplier. | - A temperature sensor has failed. | The lamp head has to be repaired. Please contact your local sales representative or Biofrontera.
Firmware of light head is faulty or missing! Please inform your supplier. | - An Update of the firmware has to be performed. | An update of the firmware has to be performed. Please contact your local sales representative or Biofrontera.

If your LED lamp no longer functions properly for some unknown reason, proceed as follows:

- Unplug the power supply for half a minute and then plug back into the outlet (This action prompts a software reboot).
- Turn the lamp back on using the touchscreen monitor and verify functionality.

Should the problem persist, please contact your sales representative or Biofrontera. The lamp may not be used until the problem has been rectified.

For all other malfunctions and difficulties with operation please contact your sales representative or Biofrontera. You will find the contact details on page 2.

9 Servicing

Servicing may only be performed by Biofrontera-authorized personnel. If servicing is done by third parties, BF-RhodoLED® warranty is void and Biofrontera cannot be held responsible for potential malfunctions or damages of the device. It is recommended to have the lamp serviced after two years.

During service, the gas springs (gas pressure springs and gas traction springs) in the scissor arm as well as the general safety condition of the BF-RhodoLED® are checked.

Contact your sales representative or Biofrontera to schedule all service appointments.

10 Maintenance and Cleaning

The device may under no circumstances be cleaned with aggressive cleaning agents or solvents (e.g. acetone or highly concentrated ethanol), as these promote wear and tear of the surface (paint coating), safety signs and graduated scale bar as well as the logo. Please avoid allowing any penetration of liquids into the lamp, BF-RhodoLED® is not waterproof and the electronics inside may be damaged.

Always unplug the lamp prior to cleaning and please observe the following cleaning practices:

Daily: | Wipe the plexiglass screen located on the bottom of the lamp head with a damp soft cloth (e. g. a microfiber cloth).
Weekly: | Wipe the entire lamp. Do not use a very wet or dripping cleaning cloth. The unit is not waterproof, and damage could occur. Weekly cleaning can be carried out using a damp cloth. If a disinfection of the device is desired, a mild disinfecting agent can be used. Most commercially available products, which are suitable for plastics, should be compatible with BF-RhodoLED®. A know exception is the agent "Incidin PlusTM" (active ingredient: Glucoprotamine) which can cause corrosion of the lamp head surfaces.; Before using a disinfection agent, always refer to its manual to check for compatibility with plastic surfaces, especially with Plexiglas.; Note: If you notice any deterioration of a surface of BF-RhodoLED after using a disinfectant, please stop further use and contact Biofrontera.
Please observe the following checks:
Monthly: | Check lamp for obvious visible damage such as damaged cables, worn off labeling, cracks on the lamp housing, etc. Do not use a damaged device for treatment and please inform your supplier.

11 Disposal Instructions

Follow all local and governmental disposal laws and regulations when disposing of the BF-RhodoLED®.

12 Technical Data

12.1 Electrical connectors

Power supply unit:

- Primary wide-range input 100-240 VAC
- Secondary safety extra-low voltage output 48 VDC
- Secondary standby voltage output 5 VDC

Mother board for voltage management and control:

- Supply voltage input 48 VDC
- Standby voltage input 5 VDC plus Standby contact
- RS485 interface
- Output supply voltage HMI board 24 VDC
- 4 x ports LED board 8-pin (2 x LED circuits, temperature (3-pin))
- 4 x connector ventilator (2-pin)

LED board:

- 2 x ports mother board 8-pin (2 x LED circuits, temperature (3-pin))

Human Machine Interface (HMI) for operation:

- Supply voltage input 24 VDC
- RS485 interface

12.2 Specification

Type | BF-RhodoLED®; Medical device class III; Device of protection class 1
Certification | UL certified
Software Version No. | 1.6_US_CAN
Service life of the lamp | Approx. 4 years
Shelf life | 1.5 years
Number of LEDs | 128
Typical peak wavelength | 635 nm ± 5 nm
Light dose (6 cm distance, 10 min) | Approx. 37 J/ cm^2
Typical irradiance | 61 mW/cm^2 +/- 15 %
Max irradiance | 77 mW/cm^2 +/- 15 % (at 5 cm treatment distance)
Illuminated area | An area of 8x18 (approx. 3.1 x 7.1 inches) cm is illuminated. The effective treatment area is 6x16 cm (approx. 2.4 x 6.3 inches).
Max. deviation of the intensity over the treatment area | Approx. 15 %
Transport and storage conditions | Temperature: -30°C to +60°C (-22°F to +140°F); Atmospheric pressure: 500 hPa - 1060 hPa Relative humidity: 10% - 90%, non-condensing
Operating conditions | Temperature: 0°C to +40°C (32°F to +104°F); Atmospheric pressure: 700 hPa - 1060 hPa Operational altitude: ≤ 2000 m above NN Relative humidity: 10% - 90%, non-condensing This PDT lamp is suitable for continuous operation.
Operating voltage | 120-240 VAC, 50/60 Hz
Output voltage | 48 VDC
Power consumption | In calibrated normal operation: approx. 140 VA; In standby mode: approx. 85 VA
Over-voltage category | II
Degree of contamination | 2
Material group (CTI) | IIIb
Protection class | IP20
Size of the lamp | 95 x 62 x 168 cm (37 x 24 x 66 inches) Devices of batch 001 to 003: 127 x 56 x 168 cm (50 x 22 x 66 inches)
Total lamp weight | Approx. 52 kg (115 lbs) Devices of batch 001 to 003: approx. 48 kg (106 lbs)

For further information please directly contact Biofrontera.
13 Labeling and Symbols

13.1 Labeling on the Lamp

The product sticker is located on the reverse side of the lamp base (see Figure 18). It contains manufacturer and product specifications (classification, serial and order number and the power supply used) as well as IP (Ingress) protection. In addition, a unique device identifier label is placed next to the product sticker.

Figure 18: Product and UDI label. (The appearance of devices from batches 001 to 003 slightly differs. Appearance and location of the labels remain unaltered.)

Labels with safety instructions, special disposal instructions and further instructions are represented in the following figures.

Figure 19: Instructions and notes on the lamp head

Figure 20: Instructions on the storage shelf. (The appearance of devices from batches 001 to 003 slightly differs. Appearance and location of the labels remain unaltered.)

Figure 21: Instructions on the scissors arm. (The appearance of devices from batches 001 to 003 slightly differs. Appearance and location of the labels remain unaltered.)

Instructions for existing ground connector connections (see Figure 22) are located:

- Next to the grounding screws, which are located within and next to the power supply cover box beneath the mobile castor, respectively
- On the power supply cover box (see Figure 23)

Figure 22: Instructions for ground connector connection

Figure 23: BF-RhodoLED®. (The appearance of devices from batches 001 to 003 slightly differs. Appearance and location of the labels remain unaltered.)

Instructions on the existing potential compensator conductor is located on the carrier bar beneath the potential compensator conductor (see Figure 24).

Figure 24: Potential compensator conductor. (The appearance of devices from batches 001 to 003 slightly differs. Appearance and location of the labels remain unaltered.)

All depicted symbols are summarized in a table in section 13.2 "Explanation of symbols".

13.2 Description of Symbols

Symbol

Description

Eye protection is required.

IP20

IP (Ingress Protection):
Protection class of the housing against contact, foreign bodies and water
2 = against ingress of solid foreign bodies ≥ 12,5 mm Ø and larger
0 = Not protected against water

Technical and electric devices must not be disposed of with household waste. Please pay attention to the applicable disposal instructions found in the user manual.

Symbol for existing ground connector connections

Follow the instructions for use!

General warning signs:

- Assembly and servicing may ONLY be performed by Biofrontera!
- Only transport lamp in the park position!
- The mobility of the extension and scissors arm may be obstructed by objects!
- Caution: heavy, do NOT lift alone.
- NEVER place this unit on an unstable, uneven surface!

Warning sign - risk of trapping fingers!

Symbol for existing potential compensation conductor
Function/Application:
The purpose of a potential compensation conductor is to connect all conducting, metallic parts of a system to each other by the protective earthing in order to achieve the same electrical potential for the connected parts. Protection against contact voltage is thus guaranteed. Releasing the potential compensation conductor is forbidden. It should be firmly fitted to the support splint.
Please observe the requirements for ME-systems set out in EN 60601-1 when using the potential compensation cable (chapter 16).

Please do not stand on or push. There is a risk that the device may fall over through of the force applied.

Please do not sit on the equipment. There is a risk that the device may fall over through the force applied.

13.3 Labeling on the Packaging

- Attention: Protect from moisture and keep dry!
- Attention: Do not throw the package, damage possible!
- Attention: Please transport and store at -30°C/ -22°F to +60°C/ 140°F, a relative humidity of 10 % to 90 % and at an atmospheric pressure of 500 hPa (50 kPa) - 1060 hPa (106 kPa).

- This side up!

- Caution, one end of the package is heavy

- Contains a lithium metal battery (optionally, not required starting from batch 007)

14 Electromagnetic compatibility (EMC)

BF-RhodoLED® meets the EMC requirements of the international standard EN60601-1-2:2015 Chapter 7 and 8. Other electrical devices can have an impact on the device. Using accessories that have not been approved can have a negative impact on the device and change the electromagnetic compatibility.
BF-RhodoLED® should not be used directly alongside or between other electrical devices.

Guidelines and manufacturer's declaration - electromagnetic emissions

BF-RhodoLED® is intended for operation in the electromagnetic environment detailed below.

The customer or operator of the device should ensure that it is operated in this environment.

Emission readings | Conformity | Electromagnetic environment - guidelines
HF emissions CISPR 11 | Group 1 | BF-RhodoLED® only uses HF energy for its internal functionality.; For this reason, its HF emission is very low and it is not likely that neighbouring electronic devices would be disturbed.
HF emissions in accordance with CISPR 11; Harmonics in accordance with IEC 61000-3-2; Voltage fluctuations/flickers in accordance with IEC 61000 3-3 | Class B; Class A; In compliance | BF-RhodoLED® is intended for operation in non-residential facilities and such like that are connected directly to a public low-voltage supply network that also supplies residential buildings.

Guidelines and manufacturer's declaration - electromagnetic immunity

BF-RhodoLED® is intended for operation in the electromagnetic environment detailed below.

The customer or operator of the device should ensure that it is operated in this environment.

Immunity tests | IEC 60601 test levels | Compliance level | Electromagnetic environment - guidelines
Static discharge in accordance with IEC 61000-4-2 | ±8 kV contact discharge ±2 kV, ±4 kV, ±8 kV and ±15 kV air discharge | ±8 kV contact discharge ±2 kV, ±4 kV, ±8 kV and ±15 kV air discharge | Floors should be made of wood or concrete or finished with ceramic tiles. If the floor is finished with synthetic material, the relative air humidity must be at least 30 %.
Fast, transient electrical disturbances/bursts in accordance with IEC 61000-4-4 | ±2 kV for mains lines ±1 kV for input and output lines | ±2 kV for mains lines | The quality of the supply voltage should correspond to that of a typical commercial or hospital environment.
Surges in accordance with IEC 61000-4-5 | ±1 kV voltage outer conductor - outer conductor ±2 kV outer conductor - earth | ±1 kV voltage outer conductor - outer conductor ±2 kV outer conductor - earth | The quality of the supply voltage should correspond to that of a typical commercial or hospital environment.
Voltage drops, brief interruptions and fluctuations in the supply voltage in accordance with IEC 61000-4-11 | 0 % UT for 0.5 cycles at phase angles of 0°, 45°, 90°, 135°, 180°, 225°, 270° and 315° (applicable only to me equipment connected to single-phase a.c. mains) 0 % UT for 1 cycle 70 % UT for 25/30 cycles 0 % UT for 250/300 cycles | 0 % UT for 0.5 cycles at phase angles of 0°, 45°, 90°, 135°, 180°, 225°, 270° and 315° (applicable only to me equipment connected to single-phase a.c. mains) 0 % UT for 1 cycle 70 % UT for 25/30 cycles 0 % UT for 250/300 cycles | The quality of the supply voltage should correspond to that of a typical commercial or hospital environment. If the operator of the device needs functionality to be maintained despite interruptions in the energy supply, it is advisable to run the device on an uninterruptable power supply or a battery.
Power frequency (50/60 Hz) magnetic field in accordance with IEC 61000-4-8 | 3 A/m | 3 A/m | Mains frequency magnetic fields should correspond to the values typically found in the commercial and hospital; environment.

Comment: UT is the mains AC voltage prior to application of the test level

Guidelines and manufacturer's declaration - electromagnetic immunity

BF-RhodoLED® is intended for operation in the electromagnetic environment detailed below. The customer or operator of the device should ensure that it is operated in this environment.

Immunity tests | IEC 60601 test levels | Compliance level | Electromagnetic environment - guidelines
Conducted HF disturbances in accordance with IEC 61000-4-6; Radiated HF disturbances in accordance with IEC 61000-4-3 | 3 V 150 kHz to 80 MHz; 6 V ISM bands 0.15 - 80 MHz 80 % AM with 1 kHz; 3 V/m 80 MHz to 2.7 GHz 80 % AM with 1 kHz | 3 V; 6 V; 3 V/m | Portable and mobile communication devices should not be used in closer proximity of the unit or its cables than the recommended safety distance of 300 mm.; Interference may occur in the vicinity of equipment marked with the following symbol.

Comment 1: These guidelines may not be applicable in all cases. The propagation of electromagnetic values is influenced by absorptions and reflections of buildings, objects, and people.

Recommended safety distances between portable and mobile HF telecommunication devices and the BF-RhodoLED®

The BF-RhodoLED® is intended for use in the electromagnetic environment in which the HF disturbances are controlled.

The customer or operator of the device can help to avoid electromagnetic interference by maintaining the minimum safe distance between portable and mobile high-frequency telecommunication devices (transmitters) and the device. Portable RF communications equipment (radios, including their accessories such as antenna cables and external antennas) should not be used at a distance less than 30 cm (or 12 inches) from the manufacturer's specified parts and leads of the BF-RhodoLED®. Failure to do so may result in a reduction in the performance of the device.

BF-RhodoLED® should not be used directly alongside or between other electrical equipment.

Guidelines and manufacturer's declaration - proximity fields from RF wireless communication equipment

BF-RhodoLED® is intended for operation in the electromagnetic environment detailed below.

The customer or operator of the device should ensure that it is operated in this environment.

Service | Frequency range/ discrete frequencies MHz | Compliance level [V/m]
TETRA 400 | 390 | 27
GMRS 460, FRS 460 | 430 | 28
LTE Band 13, 17 | 734 746 788 | 9
GSM 800/900, TETRA 800, iDEN 820, CDMA, LTE Band 5 | 821 862 948 | 28
GSM 1800, CDMA 1900, GSM 1900,DECT, LTE Band 1,3,4, 25 | 1730 1825 1970 | 28
Bluetooth, WLAN, 802.11 b/g/n, RFID 2450, LTE Band 7 | 2452 | 28
WLAN 802.11 a/n | 5240 5500 5700 | 9

Version 2.7

INSTRUCTION FOR USE

User Manual

Manufacturer: Biofrontera Pharma GmbH
Distributor: Biofrontera Inc.

Foreword

Thank you for choosing the RhodoLED® XL LED lamp for your photodynamic therapy. RhodoLED® XL has been developed in accordance with applicable technical standards to provide high energy efficiency as well as constant light emission at the desired wavelength.
Your lamp must be installed and maintained by a qualified Biofrontera technician and used only in accordance with the instructions in this manual. You may request the latest printed version covering this model from Biofrontera at any time.

Our drug Ameluz® and medical device RhodoLED® XL have been approved in combination for photodynamic therapy; the only approved use of our lamp is in combination with Ameluz® gel. This user manual provides important RhodoLED® XL product details, precautions and warnings, and operating instructions. For Ameluz®, please use its US prescribing information. The Ameluz® prescribing information includes information on how to use the gel along with contraindications, warnings and precautions and dosage and administration.

Thorough reading and use of both this user manual and the Ameluz® USPI is required prior to treatment.

Our combination Ameluz®/RhodoLED® XL for photodynamic therapy is only to be used by physicians or healthcare professionals.

For further questions about Ameluz®, RhodoLED® XL or the combination therapy please contact your sales representative or Biofrontera (Ameluz-US@biofrontera.com). See contact information below or visit us at http://www.biofrontera.us.com/

Sales representative:

Name:

Tel.:

E-mail:

Biofrontera Inc.

120 Presidential Way
Suite 330
Woburn, MA 01801
USA
Phone: (844) 426-3589

Warranty and Disclaimers
Please see the terms and conditions of your contract for this information.

Manufacturer
Biofrontera Pharma GmbH, Hemmelrather Weg 201, 51377 Leverkusen, Germany

"AMELUZ and RHODOLED are registered trademarks of Biofrontera Pharma GmbH. ©2024 Biofrontera Pharma GmbH. All rights reserved.”

1 Intended Use

RhodoLED® XL is a red light-emitting LED lamp, which is used exclusively in combination with Ameluz® gel for lesion-directed and field-directed treatment of actinic keratoses of mild-to-moderate severity on the face and scalp.

2 RhodoLED® XL - General Description

RhodoLED® XL is comprised of three main components, the lamp head, an easily adjustable spring arm, and the mobile base with castors for smooth transport. In addition, the lamp has a convenient touchscreen monitor and aids for positioning the lamp head. The device is connected to the mains via a fixed mains supply cable.

3 Warnings and Precautions

The RhodoLED® XL has been developed for use in photodynamic therapy in combination with Ameluz® gel (excitation wavelength 635 nm). Any other use or combination of use is prohibited.

During PDT side-effects such as application site erythema, pain, irritation, edema, pruritus, exfoliation, scab, induration and vesicles may occur. For further information please see Ameluz® USPI chapter 6.

The user manual must be read carefully prior to using the RhodoLED® XL.

The RhodoLED® XL may only be used by healthcare professionals who have received adequate training in its use.

Bright light, do not stare into the light source

Protective eye wear must be used by patient, healthcare providers and any persons present during the illumination period.
Do not stare in the LED beam. LEDs are classified in the exempt group according to IEC 62471:2006.

Distance sensor of RhodoLED® XL is a class 1 laser product in compliance with IEC 60825-1:2014. A class 1 laser product is safe under all conditions of normal use.

Risk of trapping fingers!
Depending on positioning, fingers can be trapped
between LED panels,
between LED panels and the holding bracket,
between the movable part and the fixed part of the lamp head holding bracket.

Neither the RhodoLED® XL nor the power supply unit should be exposed to excessive mechanical stress or serviced by unauthorized personnel. Assembly and servicing may only be carried out by Biofrontera qualified professionals.

In order to avoid the risk of electrical shock, the device may only be connected to a power supply with a grounded connection.

Neither the RhodoLED® XL nor its control unit may come into contact with water as this may lead to severe damage or electrical shock (exception: cleaning with a damp cloth).

The RhodoLED® XL should be operated and housed indoors in areas with temperatures between 59 °F and 86 °F (15 °C and 30 °C), and relative humidity of 10 % to 90 %.

Medical electronic devices require special precautionary measures with regard to the electro-magnetic compatibility (EMC); to avoid electro-magnetic disturbances, please do not place the device close to other electrical devices.

There is a risk of tripping over the power cord or the lamp base. When transporting or when device is not in use, unplug and keep the power cord rolled up.

Ensure that the control unit is always returned to parking position to avoid damage during transport.

The control unit should not be exposed to strong external pressure or sharp objects.

A person trained in operation of the RhodoLED® XL must always be present during treatment.

Before treating affected skin area with the topical medication check the proper functioning of the RhodoLED® XL. Do not use a damaged device for treatment.

RhodoLED® XL is intended for operation in non-residential facilities and such like that are connected directly to a public low-voltage supply network that also supplies residential buildings. RhodoLED® XL shall be operated in environments of professional health care facilities except in the vicinity of RF surgical equipment and outside the RF-shielded room of a magnetic resonance imaging system

The RhodoLED® XL LED panels should only be used in curved shape and not in fully unfolded form. This is necessary to ensure the application of 37 J/cm² during the illumination.

Do not place the device in such a way that it is difficult to disconnect the device's power plug from the mains during operation.

The device must be protected against unauthorized use.

Maintenance and initial set up of the RhodoLED® XL must be carried out by authorized personnel. In the event of servicing or set up being carried out by any other party, Biofrontera assumes no responsibility or liability regarding the safety or use of the device.

4 RhodoLED® XL Technical Description

4.1 Light emitting diodes (LED)

RhodoLED® XL is a red-light emitting LED lamp, comprised of three main components, the lamp head, an easily adjustable spring arm, and the mobile base with castors for smooth transport. In addition, the lamp has a convenient touchscreen monitor and aids for positioning the lamp head. RhodoLED® XL has 45 LEDs per panel with a total of 5 panels (225 LEDs), which emit a uniform, visible red light. The typical peak wavelength is approximately 635 nm with a half-band width of 16 nm.

Figure 1: LED panels with LED distribution and emission spectrum of RhodoLED® XL LEDs.

The RhodoLED® XL LEDs are calibrated such that the skin being treated receives a light dose of approximately 37 J/cm^2 under the following conditions:

- Illumination time of 13.5 minutes

- Treatment distance of 4.9 ± 0.6 inch (12.5 cm ± 1.5 cm)

The illumination area of the LED lamp is 9.06 x 11.42 inch (23 cm x 29 cm) for all panels in a curved shape.

The LEDs are distributed on each panel in a specific way (see Figure 1), such that they are more densely packed towards the upper and lower edges than in the center region of each panel. This distribution optimizes the homogeneity of illumination over the treated skin.

4.2 RhodoLED® XL Components

The RhodoLED® XL consists of the following main components (Figure 2):

- Lamp head with telescope suspension
- Spring arm
- Control unit
- Mobile base (includes support rail, castors and power supply)

Figure 2: RhodoLED® XL main components

5 Operating environment of RhodoLED® XL

RhodoLED® XL shall be operated in environments of professional health care facilities. For a detailed description in electromagnetic compatibility see chapter 15. RhodoLED® XL is intended for operation in non-residential facilities and such like that are connected directly to a public low-voltage supply network that also supplies residential buildings.
6 Eye Protection

Protective eye wear must be used by patient, healthcare providers and any persons present during the illumination period. Do not stare into the LED beam. RhodoLED® XL LEDs are classified in the exempt group product according to IEC 62471:2006. The operator and other persons present must wear protective glasses with a visible light transmission (VLT) of approximately 10 %. The patient must wear eye protection such as disposable eye protection pads or eye caps with an optical density for visible light of 6 or higher. Both options are effective and comfortable for use during treatment.

Note: Eyewear is not part of the medical device. Please carefully read any accompanying usage information before using any eye protection.

Protective eye wear must be used by patient, healthcare providers and any persons present during the illumination period.
Do not stare in the LED beam. LEDs are classified in the exempt group according to IEC 62471:2006.

7 RhodoLED® XL PDT Summarized Step-by-Step Instruction

These instructions should be used in conjunction with detailed operating instructions below (chapter 8). The section titles and numbers listed next to the instruction refer to the detailed instructions that correspond with each step.

Note: Every user of the RhodoLED® XL must be trained in operating the device. The initial training is provided by Biofrontera during set-up of the RhodoLED® XL. Recurrent training is not mandatory but can be provided by Biofrontera employees or other authorized parties. Before treating a patient with Ameluz®, please ensure that RhodoLED® XL is in good working order.

STEP 1) | Plug in the lamp.
STEP 2) | Turn on the lamp and wait for the home screen to appear (see chapter 8.4.3).
STEP 3) | Check the proper functioning of the RhodoLED® XL.
STEP 4) | Treat the affected skin area: Application, incubation, and removal of the topical medication according to the USPI of Ameluz®.
STEP 5) | Position the patient comfortably and equip the patient with protective eyewear (see chapter 6).
STEP 6) | Select active panels (see chapter 8.4.5).
STEP 7) | Position the lamp and adjust the lamp head over the skin area to be treated (distance 4.9 inch /12.5 cm) (see chapter 8.4.6).
STEP 8) | Put on protective eyewear and make sure anyone remaining in the treatment room also wears protective eyewear (see chapter 6).
STEP 9) | Start treatment by pressing Start, the illumination period begins (see chapter 8.4.9). Remind the patient to remain still throughout the illumination period. If audible indicators during treatment are activated, explain the sounds to the patient. If the patient needs a break, press Pause on the screen. To resume treatment, press Resume (see chapter 8.4.10). To abort the illumination, press Cancel (see chapter 8.4.10). Always stay with the patient during the illumination period.
STEP 10) | At the end of the illumination period, remove patient's protective eyewear and follow further instructions in the Ameluz® USPI.

8 Detailed Operating Instructions

Note: Every user of the RhodoLED® XL must be trained in operating the device. The initial training is provided by Biofrontera during set-up of the RhodoLED® XL. Recurrent training is not mandatory but can be provided by Biofrontera employees. The device must be protected against unauthorized use.

Protective eye wear must be used by patient, healthcare providers and any persons present during the illumination period.
Do not stare in the LED beam. LEDs are classified in the exempt group according to IEC 62471:2006.

8.1 Transport of RhodoLED® XL and Spring Arm Lock Function

During transportation the RhodoLED® XL must be in the transport position (see Figure 3). For the transport position the spring arm is moved down as far as possible and the locking bolt at the joint between head and spring is moved to the right (Figure 3). In this position, the spring arm is locked and cannot be moved upwards. To release the spring arm lock, push the locking bolt to the left (Figure 3). The locking function is located at the bottom of the spring arm, close to the lamp head connection.

For transport, please ensure that the control unit of RhodoLED® XL is placed on the left side (see Figure 3).

Figure 3: Transport position of RhodoLED® XL and locking function of spring arm. Locking function is located at the bottom of the spring arm, close to the lamp head connection.

8.2 Movement Areas

The swivel range of the spring arm to the left and right of the main axis is +/- 5°. The vertical range of the spring arm is 68°. The spring arm with internal gas spring allows seamless adjustment to any height. The lamp head can be rotated by 360° (Figure 4). In addition, the panels can be tilted up to 90° at the holding bracket (Figure 4).

Note: If the spring arm is at the top, it may collide with the LED panels when they are rotated 360°.

Figure 4: Rotation and tilting of the lamp head.

The orientation of the panels can be changed from a curved shape to an unfolded form by pulling the holding bracket apart (Figure 5).

Figure 5: Movement range of the lamp head.

Note: The RhodoLED® XL LED panels should only be used in curved shape and not in a fully unfolded form. This is necessary to ensure the application of 37 J/cm² during the illumination.

The control unit can be turned from the left to the right side of the device (see Figure 6). The control unit must be brought completely into the selected position until it snaps into place.

Note: If the control unit is not snapped into position, there may be a collision between the spring arm and the control unit.

Figure 6: Control unit positions

8.3 Turning RhodoLED® XL On and Off

Note: Before turning on the lamp, the power cord must be plugged in into the power grid. RhodoLED® XL is intended for operation in non-residential facilities and such like that are connected directly to a public low-voltage supply network that also supplies residential buildings.

Note: Do not place the device in such a way that it is difficult to disconnect the device's power plug from the mains during operation.

The RhodoLED® XL is equipped with a cable winding system. To unwind the cable, pull the plug out of the opening of the lamp base. When the cable is being unwound, a clicking sound is heard. The power button is located on the right side of the control unit. With the lamp plugged in, press the power button to start the device.

To power down the device, press the power button and the device shuts down. RhodoLED® XL can also be switched off via the software. To switch the device off, press the software power button in the upper right corner. To rewind the cable, remove the plug from the wall socket and slightly pull on the cable once. Hold the cable loosely in your hand to allow rewinding. The cable winder will pull the cable in automatically until it is fully rolled up. Do not completely release the cable when winding it up to avoid damage of the device.

Figure 7: Control unit of RhodoLED® XL with power button

8.4 RhodoLED® XL Controls

8.4.1 Control Unit

The touchscreen of the control unit can be used while wearing commercially available examination gloves.

8.4.2 Splash Screen

The Biofrontera corporate logo and software version are displayed during the LED lamp operating system start-up (Figure 8). The operating system takes approximately 10 seconds to load.

Figure 8: Splash screen

8.4.3 Home Screen

The home screen appears after the operating system has loaded.

Figure 9: Home screen

8.4.4 The Treatment Profile

The RhodoLED® XL has a fixed LED light intensity which ensures the application of 37 J/cm² within the 13.5-minute treatment time.

8.4.5 Selecting Active LED Panels

The device has 5 LED panels which are also displayed by the software (Figure 10). The illustrated panels are visible from the back side and the corresponding panel of the device can be identified via the handles, starting from the left. All panels are activated by default and can be deactivated via the software. To deactivate LED panels, press on the illustrated panel. For easier orientation, the panel number can also be found at the backside of the respective panel (Figure 11).

Figure 10: Software illustration of RhodoLED® XL LED panels (all panels are activated)

Figure 11: Panel number at the backside of the panel

Deactivated panels are displayed in grey with a power symbol in their centers (Figure 12). Activated panels are highlighted and the current distance to the treatment area is displayed.

Figure 12: Coloring of a switched off panel

8.4.6 Treatment Area

The illumination area of RhodoLED® XL is 9.06 x 11.42 inch (23 cm x 29 cm) when all panels are arranged in the standard curved shape. This usually allows a full-face illumination. However, face and head sizes are subject to strong variations between patients. As a rough guidance, the midlines of the outer two panels marks the outer boundaries of the illumination area (see Figure 13 as guidance).

Note: The RhodoLED® XL LED panels should only be used in curved shape and not in fully unfolded form. This is necessary to ensure the application of 37 J/cm² during the illumination.

Figure 13: Treatment area of RhodoLED® XL from the side and in top view.

Note: If less than 5 panels are used for a treatment, it must be ensured that at least three adjacent panels are used. The treatment area is thereby reduced and reaches from the midline of the one outer panel to the other midline of the other outer panel.

If a treatment with less than 5 active LED panels is started, a message dialog appears which must be confirmed.

8.4.7 Adjusting the Treatment Distance

The correct treatment distance for the RhodoLED® XL is 4.9 ± 0.6 inch (12.5 ± 1.5 cm). Each LED panel is equipped with a distance sensor to allow individual adjustment of all panels. The distance sensor is automatically switched on if the panel is switched on. The current distance of each panel is shown on the control unit display above the panel illustration. The following table summarizes the visualization of the treatment distance.

Note: When starting the treatment, the LED panels that are too close or too far away from the treatment area will nevertheless also light up. To disable an LED panel during the treatment it must be switched off on the display (see Figure 12).

Table 1: Adjusting the treatment distance

Pictogram | Meaning
 | Treatment distance is correct for this LED panel (4.9 ± 0.6 inch / 12.5 ± 1.5 cm), adjustment light is/turns on
 | Treatment distance is too small for this LED panel. LED panel must be further away from treatment area, adjustment light is/turns off
 | Treatment distance is too large for this LED panel. LED panel must be closer to the treatment area, adjustment light is/turns off
 | This LED panel is switched off

8.4.8 Adjustment Light

If the correct treatment distance of 4.9 inch (12.5 cm) is set the LEDs of the panel light up at a low light intensity to allow an easy adjustment of the distance and the target treatment area.

The size of the treatment area is 9.06 x 11.42 inch (23 cm x 29 cm) for all panels in a curved shape.

Note: When starting the treatment, the LED panels that are too close or too far away from the treatment area will nevertheless also light up. To disable an LED panel during the treatment it must be switched off on the display (see Figure 12).

Figure 14: Low light intensity for correct adjustment of LED panels.

8.4.9 Starting an Illumination

To start a treatment, press the Start button. Before starting the treatment make sure every person present wears the correct eye protection (see chapter 6) and confirm the query for eye protection (Figure 15).

Protective eye wear must be used by patient, healthcare providers and any persons present during the illumination period.
Do not stare in the LED beam. LEDs are classified in the exempt group according to IEC 62471:2006.

Figure 15: Note on eye protection before starting treatment.

During the illumination, the remaining treatment time is displayed in the diagram. The progress is marked green in the profile and with a green dotted vertical line (Figure 16).

Figure 16: Treatment progress.

8.4.10 Pause, continue, or cancel a treatment

Figure 17: Pause, continue, and cancel a treatment.

To abort the current treatment, press the Cancel button. The applied light dose and the remaining treatment time is displayed in a query. Confirm the query to cancel the treatment (Figure 18).

Figure 18: Cancelled treatment message shows applied light dose and remaining treatment time.

Note: If you cancel prior to the end of the total treatment time, the internal timer will reset. The remaining treatment time will not be saved.

After pressing Cancel and Yes or upon completion of the treatment the software will automatically return to the home screen.

8.4.11 Audio Signals After Treatment

After completion of the treatment a signal occurs, and the lamp will stop the illumination. Audio signals can be deactivated via the settings menu (see chapter 8.5.4).

Further audio signals occur for queries that must be confirmed and may occur in the event of an error. A description of possible errors can be found in chapter 9.

8.5 Settings Menu

To open the settings menu, select the gear symbol in the upper right corner of the screen.

The settings menu is organized in the tabs General, Service and Info.

Figure 19: The settings menu is organized in the three main tabs General, Service and Info

8.5.1 Language

Language settings are part of the General settings tab. Select a language by tapping on the left and right arrows. The software provides the languages English, Spanish and German.

Confirm the selected language by pressing the Save button, to discard the settings leave the menu without pressing Save.

8.5.2 Distance Units

Unit settings are part of the General settings tab. The distance of the LED panels to the treatment area can be displayed in inch or in cm. Select a distance unit by tapping on the arrows.

Confirm the selected distance unit by pressing the Save button, to discard the settings leave the menu without pressing Save.

8.5.3 Auto power off

Auto power off settings are part of the General settings tab. The auto power off setting is used to set the time after which the lamp is automatically switched off. Values of 15, 30, 60 and 120 minutes can be selected.

Confirm your selected auto power off time by pressing Save, to discard the settings leave the menu without pressing Save.

8.5.4 Sound Settings

Sound settings are part of the General settings tab. Activate and deactivate the audio signals for typing and sounds during the treatment. To do this, activate or deactivate the corresponding sliding switch. A green slider means the sound is currently switched on.

Confirm your selection by pressing Save, to discard the settings leave the menu without pressing Save.

Note: Warning sounds will be emitted if an error occurs during operation of the lamp. Warning sounds cannot be turned off.

8.5.5 Info-Tab

The system status provides information about the current hardware and software status of the device.

This includes information about:

• The serial numbers of the systems core components
• Automatic switch off settings
• Software version
• List of occurred errors (chapter 9)

Note: In case of a malfunction of the device, please have this information available.

8.5.6 Service Menu

Authorization is required to access the service menu. Only authorized personnel can access the service menu. See also chapter 10.

9 Error Messages

The RhodoLED® XL has an integrated monitoring function. In the event of a malfunction, an error message will appear in the message display. Possible error messages are set out in the table below. Please ensure that you always correctly record the error code when contacting Biofrontera customer service in case of an error message.

Note: even if usage of the lamp is still possible in case of an error, please contact your local sales representative or Biofrontera if an error message persists.

Error code | Possible causes | Measures
001 System error | Error in system of the device | - Confirm the system error - Please contact your local sales representative or Biofrontera
002 Communication error | Communication between the control unit and the LED panels disturbed | - Confirm the communication error - Treatment can be continued by confirming the message dialog - Please contact your local sales representative or Biofrontera - If there is a permanent error in the communication, no further treatment is possible
003 Panel error | Error in the control of one or more LED panel Defective LED panels are marked with a red triangle | - Confirm the Panel error - Treatment can be continued by confirming the message dialog - Please contact your local sales representative or Biofrontera
004 Distance sensor error | Error in control of the distance sensors | - Confirm the Distance sensor error - Treatment can be continued by confirming the message dialog - Please contact your local sales representative or Biofrontera
005 Update process error | The software needs updating | - Please contact your local sales representative or Biofrontera
006 Temperature sensor error | Defective temperature sensor of defect in temperature sensor control | - Confirm the Distance sensor error - Treatment can be continued by confirming the message dialog - Please contact your local sales representative or Biofrontera
007 Cooling system error | The ventilators or ventilator slots are blocked The air inlets or outlets are adversely affected | - Check the ventilators and test the air inlets and outlets; - Remove any visible foreign objects which may be present - In case of continuing impairment of the cooling system, please contact your local sales representative or Biofrontera
The treatment is paused due to an overheated LED panel. Wait until normal temperature is reached. | The temperature is too high | - Wait until the standard temperature has been reached; - Treatment can then be resumed

If your RhodoLED® XL no longer functions properly for some unknown reason, proceed as follows:

- Unplug the power supply for half a minute and then plug back into the outlet (This action prompts a software reboot).
- Turn the lamp back on using the control unit and verify functionality.

Should the problem persist, please contact your sales representative or Biofrontera. The lamp may not be used until the problem has been rectified.

For all other malfunctions and difficulties with operation please contact your sales representative or Biofrontera. You will find the contact details on page 2 of the manual.

Please have the system status (chapter 8.5.5) available if you contact your sales representative or Biofrontera.

10 Servicing and repairs

Servicing and repairs may only be performed by Biofrontera-authorized personnel. For RhodoLED® XL no spare parts for replacement by the user are available.

Device is not serviced while in use with patients.

If servicing or repairs are done by third parties, RhodoLED® XL warranty is void and Biofrontera cannot be held responsible for potential malfunctions of or damages to the device or the patients.

Figure 20: Servicing and maintenance may only be performed by Biofrontera

11 Maintenance and Cleaning

The device may under no circumstances be cleaned with aggressive cleaning agents or solvents (e.g. acetone or highly concentrated ethanol), as these promote wear and tear of the surface (paint coating) and labeling. Please use only a damp cloth when wiping over the labels.

Please avoid allowing any penetration of liquids into the lamp, RhodoLED® XL is not waterproof and the electronics inside may be damaged. Do not maintain or clean the device while in use with patients.

Always unplug the lamp prior to cleaning and please observe the following cleaning practices:

Daily: | Wipe the plexiglass screen located on the bottom of the lamp head with a damp soft cloth (e. g. a microfiber cloth).
Weekly: | Wipe the entire lamp. Do not use a very wet or dripping cleaning cloth. The unit is not waterproof and damage could occur. Weekly cleaning can be carried out using a damp cloth or Multi-Purpose Cleaners (Clorox Healthcare VersaSure Wipes).
Please observe the following checks:
Monthly: | Check lamp for obvious visible damage such as damaged cables, worn off labeling, cracks on the lamp housing, etc.; Do not use a damaged device for treatment and please inform your supplier.

12 Disposal Instructions

Follow all local and governmental disposal laws and regulations when disposing of the RhodoLED® XL.

13 Technical Data

13.1 Electrical Connectors

Power supply unit:

- Primary wide-range input 100-120 VAC
- Secondary safety extra-low voltage output 48 VDC
- Secondary standby voltage output 5 VDC

LED controller board:

- Supply voltage input 48 VDC
- 2x CAN interface (2 pin)
- LED board FFC (12 pin)
- Distance sensor FFC (4 pin)
- 2 x connector ventilator (3 pin)

LED board:

- LED controller board FFC 12 pin (3 x LED circuits, temperature)
- Distance sensor FFC (4 pin)

Human Machine Interface (HMI) for operation:

- Supply voltage input 48 VDC (2 pin)
- Secondary standby voltage input 5 VDC (4 pin)
- CAN interface (3 pin)
- USB interface (5 pin, covered)
- Speaker (2 pin)
- Touch controller (4 pin)
- Display data LVDS (40 pin)
- On/off switch (2 pin)
- HMI module to pillar external connector (10 pin)
- Grounding (1 pin)

13.2 Specification

Type | RhodoLED® XL; Medical device class III; Device of protection class 1
Certification | UL certified E513735
Software Version No. | g2.13.00.3840
Service interval | Biofrontera recommends performing service every 2 years
Number of LEDs | 225
Typical peak wavelength | 635 nm ± 5 nm
Light dose | Approx. 37 J/ cm^2 at 4.9 inch (12.5 cm) distance, 13.5 min
Typical irradiance | approx. 46 mW/cm² ± 20 % at 4.9 inch (12.5 cm) distance
Max irradiance | approx. 55 mW/cm² at 4.9 inch (12.5 cm) distance
Illuminated area | An area of 9.06 x 11.42 inch (23 cm x 29 cm) is illuminated using all panels in curved shape.
Max. deviation of the intensity over the treatment area | Approx. 20 %
Treatment distance | 4.9 ± 0.6 inch (12.5 cm ± 1.5 cm) Measuring accuracy ± 0.3 cm (0.1 inch)
Transport conditions | Temperature: -4 °F to +140 °F (-20 °C to +60 °C) Atmospheric pressure: 500 hPa - 1060 hPa Relative humidity: 10 % - 90 %, non-condensing
Storage conditions | Temperature: +59 °F to +95 °F (+ 15 °C to +35 °C) Atmospheric pressure: 500 hPa - 1060 hPa Relative humidity: 10 % - 90 %, non-condensing Maximum storage time 180 days
Operating conditions | Temperature: +59 °F to +86 °F (+15 °C to + 30 °C) Atmospheric pressure: 500 hPa - 1060 hPa Operational altitude: ≤ 4800 m above NN Relative humidity: 10 % - 90 %, non-condensing. RhodoLED® XL must be operated in environments of professional healthcare facilities.
Operating voltage | 100-120 VAC, 60 Hz
Output voltage | 48 VDC
Power consumption | In normal operation: approx. 750 VA In standby mode: approx. 85 VA
Over-voltage category | II
Degree of contamination | 2
Material group (CTI) | IIIb
Protection class | IP20
Size of the lamp | Height 5.76 ft (175.5 cm) Width: 2.51 ft (76.4 cm) Depth: 3.19 ft (97.1 cm)
Total lamp weight | 165 lb. (75 kg)

For further information please directly contact Biofrontera.
14 Labeling and Symbols

14.1 Label on the Lamp Base

Figure 21: Product label (serial number and date of manufacturing vary) with UDI code of RhodoLED® XL on lamp base, individual code depends on the serial number and date of manufacturing of the device.

Figure 22: No stepping on the device, no disposal in household waste, information on setup and service.

Figure 23: Instruction for ground connector connection (not visible from the outside)

14.2 Label on LED Panels

Figure 24: Instruction and notes on the LED panels

Figure 25: LED Panel numbering from Panel 1 to Panel 5

14.3 Description of Symbols

Symbol

Description

Eye protection is required.

Distance sensor of RhodoLED® XL is a class 1 laser product. A class 1 laser product is safe under all conditions of normal use.

IP20

IP (Ingress Protection):
Protection class of the housing against contact, foreign bodies and water
2 = against ingress of solid foreign bodies ≥ 12,5 mm Ø and larger
0 = Not protected against water

Technical and electric devices must not be disposed of with household waste. Please pay attention to the applicable disposal instructions found in the user manual.

Symbol for existing ground connector connections

Follow the instructions for use!

General warning signs:

- Assembly and servicing may ONLY be performed by Biofrontera
- Only transport lamp in the park position
- Caution: heavy, do NOT lift alone.

Warning sign - risk of trapping fingers!

Bright light, do not stare into the light source

Do not step on the device.

15 Electromagnetic compatibility

RhodoLED® XL complies with the EMC requirements of IEC 60601-1-2:2014 + A1:2020. Other electrical devices can influence the device.

The use of accessories, transducers and cables other than those specified or provided by the manufacturer may result in increased electromagnetic emissions or reduced electromagnetic immunity of the equipment and may lead to incorrect operation. Assembly, service and repairs may only be performed by Biofrontera.

Guidelines and manufacturer's declaration - electromagnetic emissions
RhodoLED® XL is intended for operation in the electromagnetic environment detailed below.
The customer or operator of the device should ensure that it is operated in this environment.
The emission characteristics of RhodoLED® XL allow its use in industrial and hospital and healthcare professional environments (CISPR 11, Class A). When used in a residential environment (for which CISPR 11 normally requires Class B), this device may not provide adequate protection of radio services. The user may need to take corrective action by moving or repositioning the device.
Emission readings | Conformity | Electromagnetic environment - guidelines
HF emissions CISPR 11 | Group 1 | RhodoLED® XL only uses HF energy for its internal functionality. For this reason, its HF emission is very low and it is not likely that neighboring electronic devices would be disturbed.
HF emissions in accordance with CISPR 11 | Class A | RhodoLED® XL is intended for operation in non-residential facilities and such like that are connected directly to a public low-voltage supply network that also supplies residential buildings.
Harmonics in accordance with IEC 61000-3-2 | Class A | RhodoLED® XL is intended for operation in non-residential facilities and such like that are connected directly to a public low-voltage supply network that also supplies residential buildings.
Voltage fluctuations/flickers in accordance with IEC 61000-3-3 | In compliance | RhodoLED® XL is intended for operation in non-residential facilities and such like that are connected directly to a public low-voltage supply network that also supplies residential buildings.

Guidelines and manufacturer's declaration - electromagnetic immunity
RhodoLED® XL is intended for operation in the electromagnetic environment detailed below. The customer or operator of the device should ensure that it is operated in this environment.
Immunity tests | IEC 60601 test levels | Compliance level | Electromagnetic environment - guidelines
Static discharge in accordance with IEC 61000-4-2 | ±8 kV contact discharge ±2 kV, ±4 kV, ±8 kV and ±15 kV air discharge | ±8 kV contact discharge ±2 kV, ±4 kV, ±8 kV and ±15 kV air discharge | Floors should be made of wood or concrete or finished with ceramic tiles. If the floor is finished with synthetic material, the relative air humidity must be at least 30 %.
Fast, transient electrical disturbances/bursts in accordance with IEC 61000-4-4 | ±2 kV for mains lines 100 kHz repetition frequency | ±2 kV for mains lines | The quality of the supply voltage should correspond to that of a typical commercial or hospital environment.
Surges in accordance with IEC 61000-4-5 | ±1 kV voltage outer conductor - outer conductor ±2 kV outer conductor - earth | ±1 kV voltage outer conductor - outer conductor ±2 kV outer conductor - earth | The quality of the supply voltage should correspond to that of a typical commercial or hospital environment.
Voltage dips, brief interruptions and fluctuations in the supply voltage in accordance with IEC 61000-4-11 | 0 % UT for 0.5 cycles at phase angles of 0°, 45°, 90°, 135°, 180°, 225°, 270° and 315° (applicable only to me equipment connected to single-phase a.c. mains) 0 % UT for 1 cycle 70 % UT for 25/30 cycles 0 % UT for 250/300 cycles | 0 % UT for 0.5 cycles at phase angles of 0°, 45°, 90°, 135°, 180°, 225°, 270° and 315° (applicable only to me equipment connected to single-phase a.c. mains) 0 % UT for 1 cycle 70 % UT for 25/30 cycles 0 % UT for 250/300 cycles | The quality of the supply voltage should correspond to that of a typical commercial or hospital environment. If the operator of the device needs functionality to be maintained despite interruptions in the energy supply, it is advisable to run the device on an uninterruptable power supply or a battery.
Power frequency (50/60 Hz) magnetic field in accordance with IEC 61000-4-8 | 30 A/m | 30 A/m | Mains frequency magnetic fields should correspond to the values typically found in the commercial and hospital environment.
Comment: UT is the mains AC voltage prior to application of the test level

Guidelines and manufacturer's declaration - electromagnetic immunity
RhodoLED® XL is intended for operation in the electromagnetic environment detailed below. The customer or operator of the device should ensure that it is operated in this environment.
Immunity tests | IEC 60601 test levels | Compliance level | Electromagnetic environment - guidelines
Conducted HF disturbances; in accordance; with IEC 61000-4-6 | 3 V; 150 kHz to 80 MHz; 6 V ISM bands 0.15 - 80 MHz 80 % AM with 1 kHz | 3 V; 6 V | Portable and mobile communication devices should not be used in closer proximity of the unit or its cables than the recommended safety distance of 300 mm.
Radiated HF disturbances; in accordance; with IEC 61000-4-3 | 3 V/m 80 MHz to 2.7 GHz 80 % AM with 1 kHz | 3 V/m | Interference may occur in the vicinity of equipment marked with the following symbol.
Comment 1: These guidelines may not be applicable in all cases. The propagation of electromagnetic values is influenced by absorptions and reflections of buildings, objects, and people.

Recommended safety distances between portable and mobile HF telecommunication devices and the RhodoLED® XL.

Portable RF communications equipment (radios, including their accessories such as antenna cables and external antennas) should not be used at a distance less than 30 cm (or 12 inch) from the manufacturer's specified parts and leads of the RhodoLED® XL. Failure to do so may result in a reduction in the performance of the device.
RhodoLED® XL should not be used directly alongside or between other electrical equipment.

Guidelines and manufacturer’s declaration – proximity fields from RF wireless communication equipment
RhodoLED® XL is intended for operation in the electromagnetic environment detailed below. The customer or operator of the device should ensure that it is operated in this environment.
Service | Frequency range/ discrete frequencies MHz | Compliance level [V/m]
TETRA 400 | 385 | 27
GMRS 460, FRS 460 | 450 | 29
LTE Band 13, 17 | 710 745 780 | 9
GSM 800/900, TETRA 800, iDEN 820, CDMA, LTE Band 5 | 810 870 930 | 28
GSM 1800, CDMA 1900, GSM 1900,DECT, LTE Band 1,3,4, 25 | 1720 1845 1970 | 28
Bluetooth, WLAN, 802.11 b/g/n, RFID 2450, LTE Band 7 | 2450 | 28
WLAN 802.11 a/n | 5240 5500 5785 | 9

Version 1.9 SW_G2

PRINCIPAL DISPLAY PANEL – OUTER PACKAGING

Outer Packaging, single Carton

NDC 70621-101-10

Ameluz® Rx Only

(aminolevulinic acid HCl) topical gel, 10%

Use contents within 3 months after opening. Discard after: __/ __/ __.

Store refrigerated 2°-8°C (36°-46°F), excursions permitted to 15°-30°C (59°-86°F).

Keep out of the sight and reach of children.

See package insert for dosage information. Net Wt. 2 g

Distributed By: Biofrontera Inc.

660 Main Street, 1st Floor

Woburn, MA 01801

Product of Switzerland

For Topical Use Only with BF-RhodoLED® or RhodoLED® XL lamp

Healthcare Professionals Only

Ingredients: Each gram of Ameluz Gel contains 100 mg of the active ingredient, aminolevulinic acid hydrochloride (equivalent to 78 mg of aminolevulinic acid) and the following inactive ingredients: xanthan gum, soybean phosphatidylcholine, polysorbate 80, medium-chain triglyceride, isopropyl alcohol, dibasic sodium phosphate, monobasic sodium phosphate, sodium benzoate and purified water

Outer Packaging, Physician's Sample

NDC 70621-101-30

Ameluz® Rx Only

Physician's Sample

Not for sale

(aminolevulinic acid HCl) topical gel, 10%

Use contents within 3 months after opening. Discard after: __/ __/ __.

Store refrigerated 2°-8°C (36°-46°F), excursions permitted to 15°-30°C (59°-86°F).

Keep out of the sight and reach of children.

See package insert for dosage information. Net Wt. 2 g

Distributed By: Biofrontera Inc.

660 Main Street, 1st Floor

Woburn, MA 01801

Product of Switzerland

For Topical Use Only with BF-RhodoLED® lamp or RhodoLED® XL lamp

Healthcare Professionals Only

Ingredients: Each gram of Ameluz Gel contains 100 mg of the active ingredient, aminolevulinic acid hydrochloride (equivalent to 78 mg of aminolevulinic acid) and the following inactive ingredients: xanthan gum, soybean phosphatidylcholine, polysorbate 80, medium-chain triglyceride, isopropyl alcohol, dibasic sodium phosphate, monobasic sodium phosphate, sodium benzoate and purified water

Outer Packaging, Multipack

10 tubes with Net Wt. 2g each NDC 70621-101-20

Ameluz® Rx Only

(aminolevulinic acid HCl) topical gel, 10%

For Topical Use Only with BF-RhodoLED® lamp or RhodoLED® XL lamp

Healthcare Professionals Only

See package insert for dosage information.

Distributed By: Biofrontera Inc.

660 Main Street, 1st Floor

Woburn, MA 01801

Product of Switzerland

10 tubes with Net Wt. 2g each NDC 70621-101-20

Ameluz® Rx Only

(aminolevulinic acid HCl) topical gel, 10%

Use contents within 3 months after opening the individual tube.

Place the enclosed Discard after: __/ __/ __.tag on tube once opened.

Store refrigerated 2°-8°C (36°-46°F), excursions permitted to 15°-30°C (59°-86°F).

Keep out of the sight and reach of children.

See package insert for dosage information.

Ingredients:
Each gram of Ameluz Gel contains 100 mg of the active ingredient, aminolevulinic acid hydrochloride (equivalent to 78 mg of aminolevulinic acid) and the following inactive ingredients: xanthan gum, soybean phosphatidylcholine, polysorbate 80, medium-chain triglyceride, isopropyl alcohol, dibasic sodium phosphate, monobasic sodium phosphate, sodium benzoate and purified water

Distributed By: Biofrontera Inc.

660 Main Street, 1st Floor

Woburn, MA 01801

Product of Switzerland